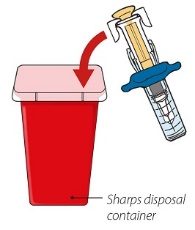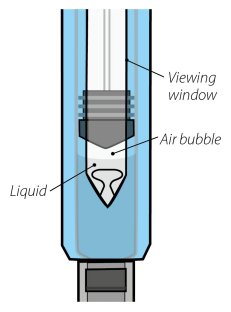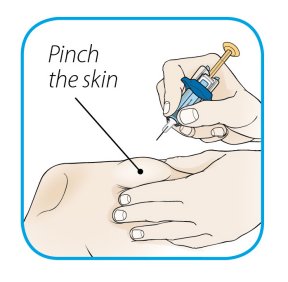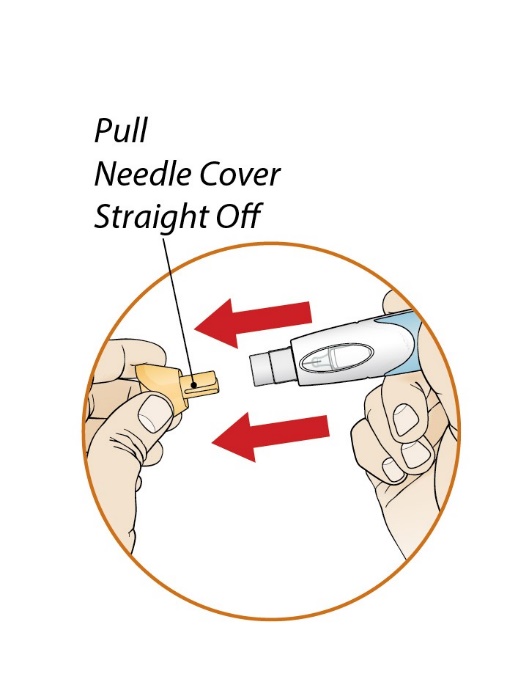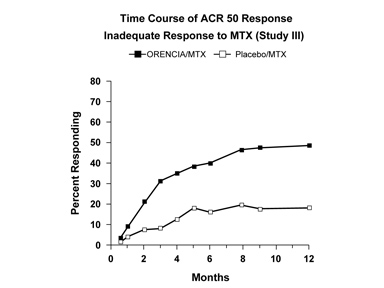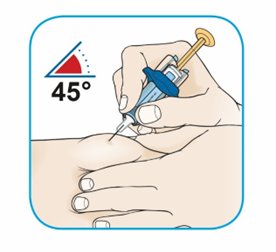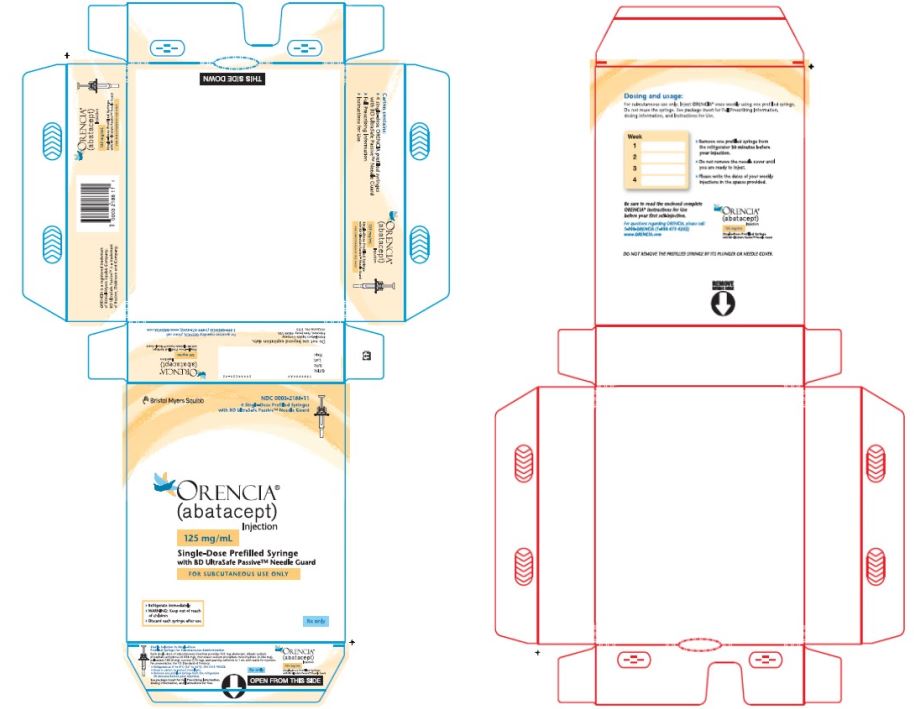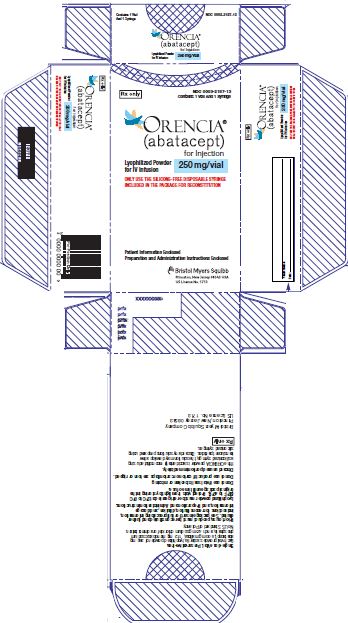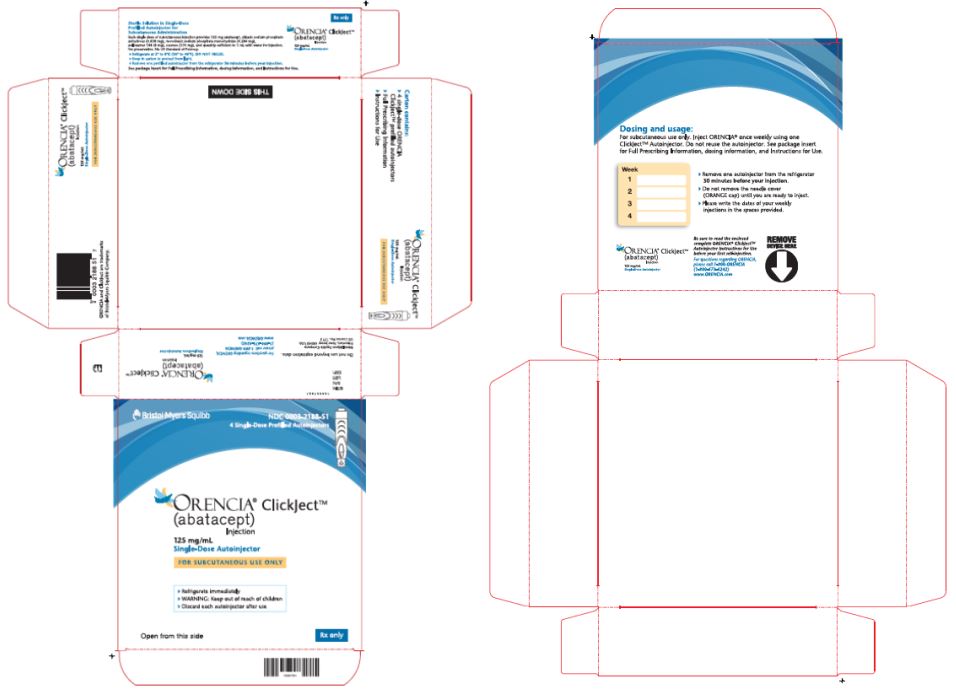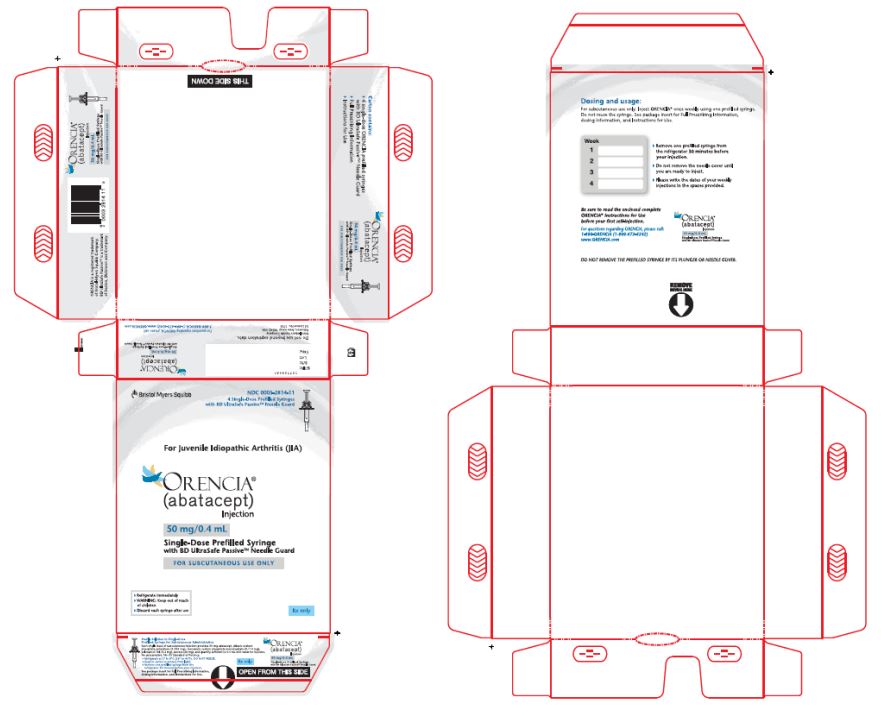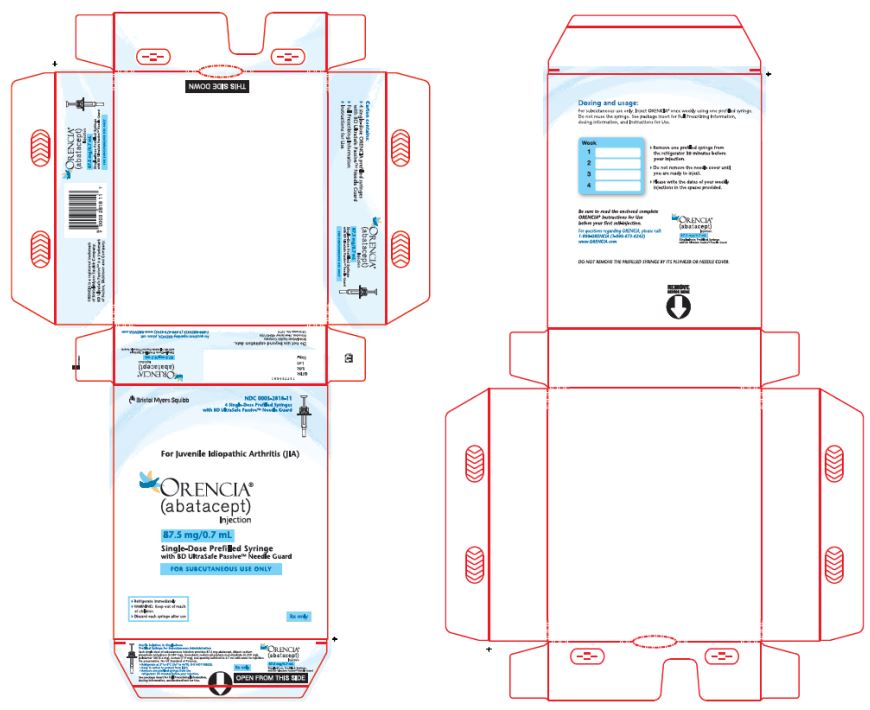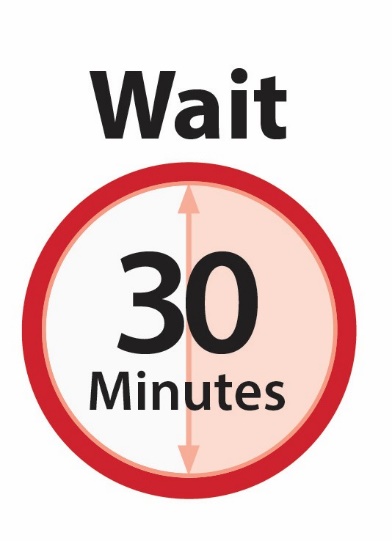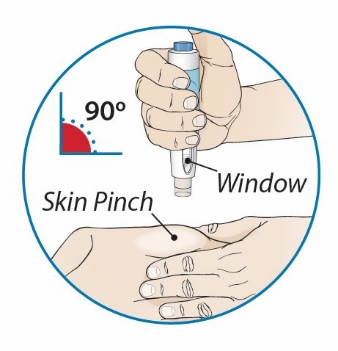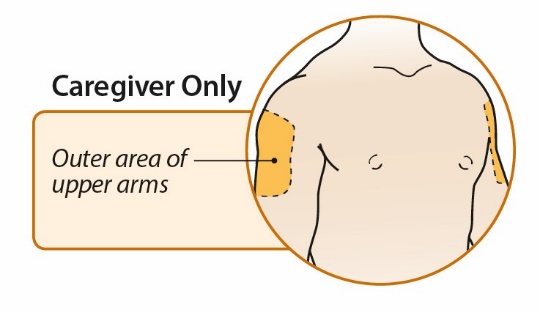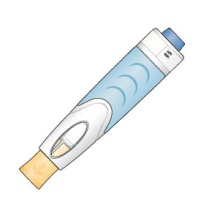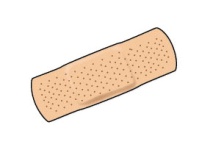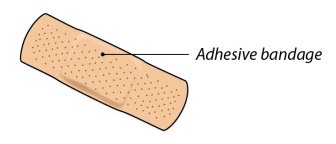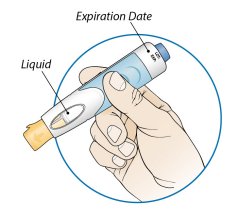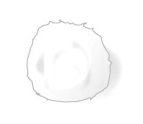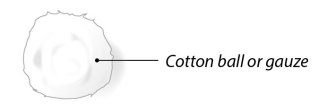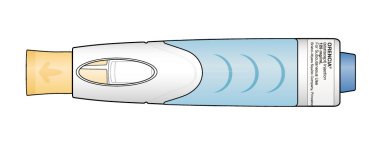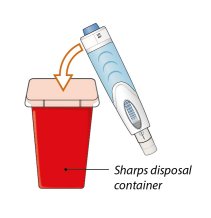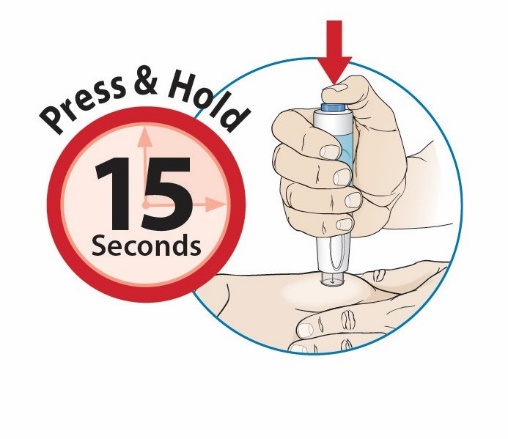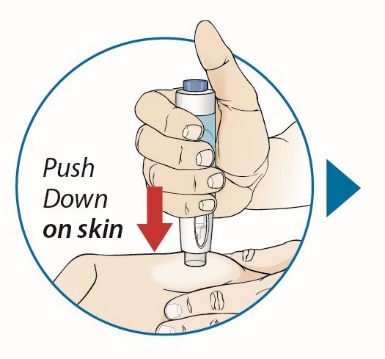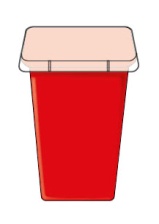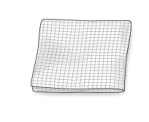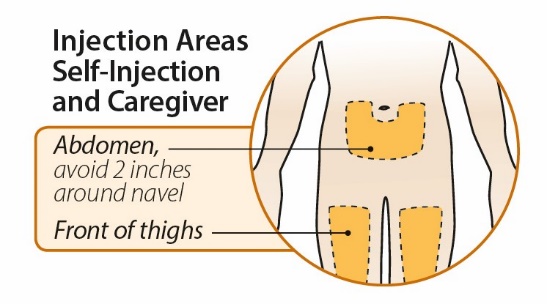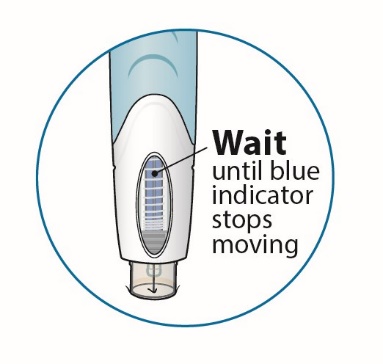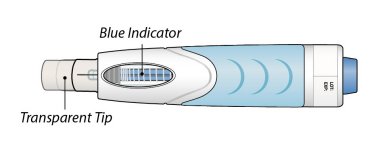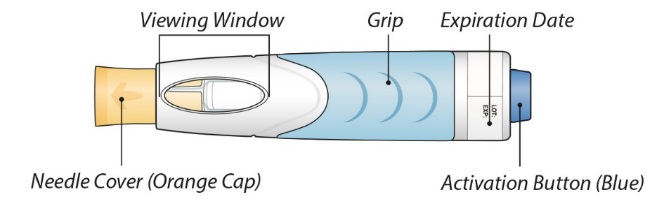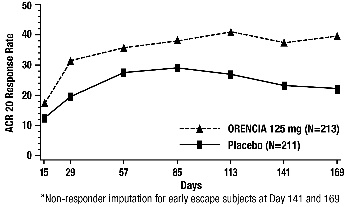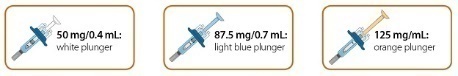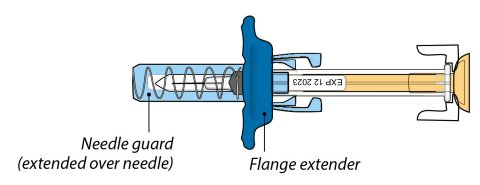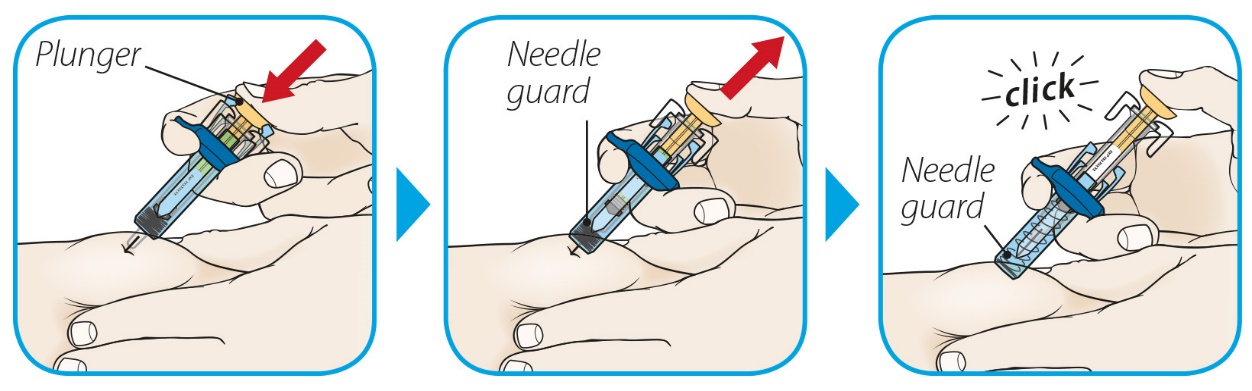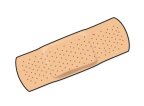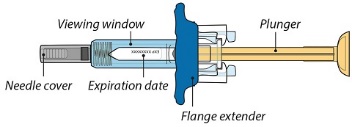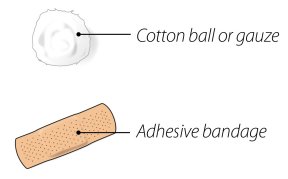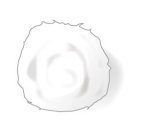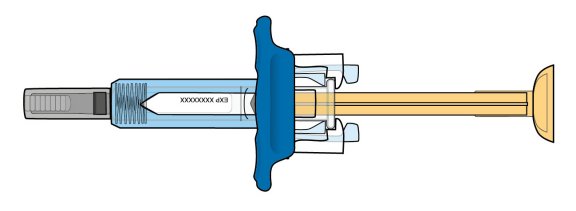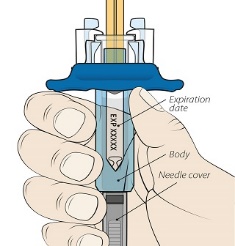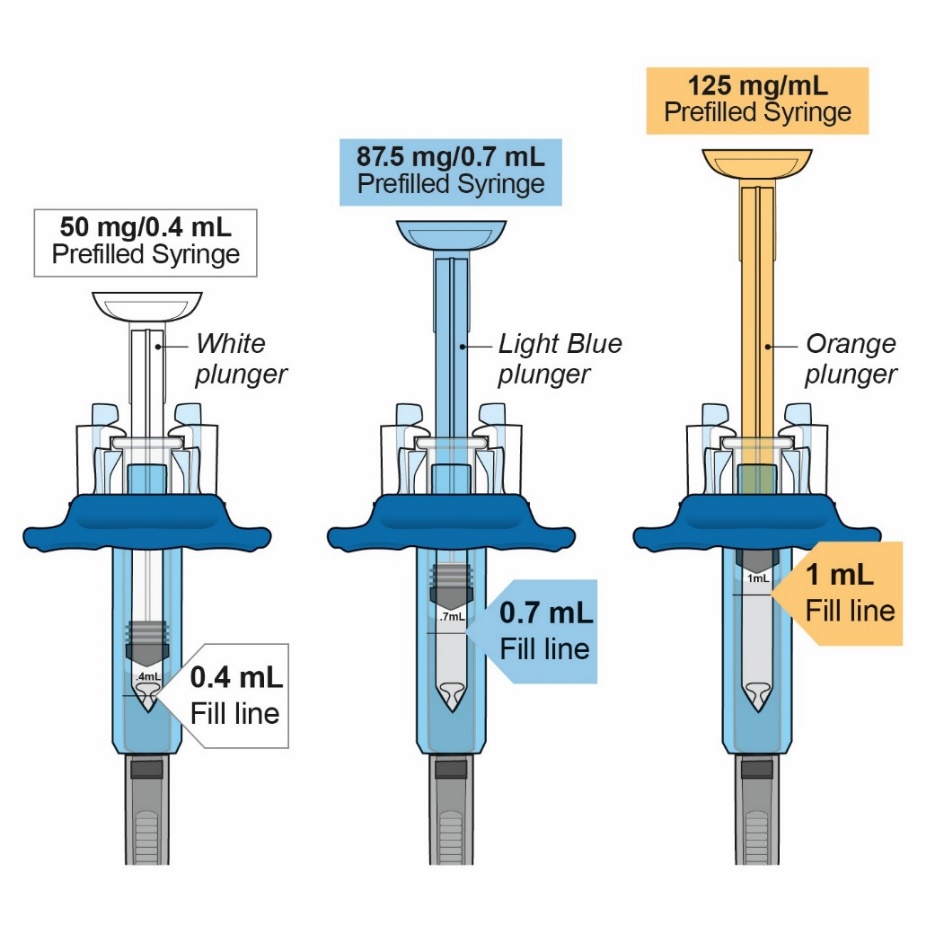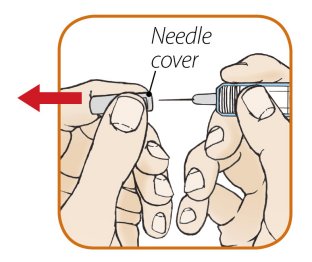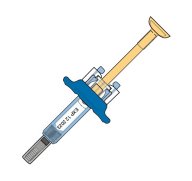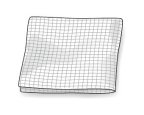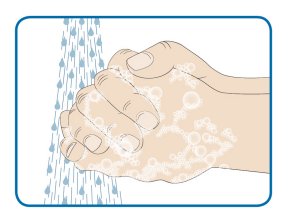 DRUG LABEL: ORENCIA
NDC: 0003-2187 | Form: INJECTION, POWDER, LYOPHILIZED, FOR SOLUTION
Manufacturer: E.R. Squibb & Sons, L.L.C.
Category: prescription | Type: HUMAN PRESCRIPTION DRUG LABEL
Date: 20251113

ACTIVE INGREDIENTS: abatacept 250 mg/15 mL
INACTIVE INGREDIENTS: maltose monohydrate 500 mg/15 mL; SODIUM PHOSPHATE, MONOBASIC, UNSPECIFIED FORM 17.2 mg/15 mL; sodium chloride 14.6 mg/15 mL

HIGHLIGHTS OF PRESCRIBING INFORMATION

These highlights do not include all the information needed to use ORENCIA safely and effectively. See full prescribing information for ORENCIA.
ORENCIA (abatacept) for injection, for intravenous use
ORENCIA (abatacept) injection, for subcutaneous use
Initial U.S. Approval: 2005

1 INDICATIONS AND USAGE

ORENCIA is a selective T cell costimulation modulator indicated for:

- the treatment of adult patients with moderately to severely active rheumatoid arthritis (RA). (1.1)
- the treatment of patients 2 years of age and older with moderately to severely active polyarticular juvenile idiopathic arthritis (pJIA). (1.2)
- the treatment of patients 2 years of age and older with active psoriatic arthritis (PsA). (1.3)
- the prophylaxis of acute graft versus host disease (aGVHD), in combination with a calcineurin inhibitor and methotrexate, in adults and pediatric patients 2 years of age and older undergoing hematopoietic stem cell transplantation (HSCT) from a matched or 1 allele-mismatched unrelated donor. (1.4)

Limitations of Use:

Concomitant use of ORENCIA with other immunosuppressives [e.g., biologic disease-modifying antirheumatic drugs (bDMARDS), Janus kinase (JAK) inhibitors] is not recommended. (1.5, 5.1)

2 DOSAGE AND ADMINISTRATION

Intravenous Use for Adult RA (2.1) and Adult PsA (2.3)

- Administer at 0, 2, and 4 weeks, and every 4 weeks thereafter, as a 30-minute infusion

Body Weight of Patient | Dose | Number of Vials
Less than 60 kg | 500 mg | 2
60 to 100 kg | 750 mg | 3
More than 100 kg | 1,000 mg | 4

Subcutaneous Use for Adult RA (2.1)

- Prior to the first subcutaneous dose, may administer an optional loading dose as a single intravenous infusion as per body weight categories above.
- Administer 125 mg by subcutaneous injection once weekly (within a day of the intravenous infusion if infusion given).
- Patients switching from intravenous use to subcutaneous use, administer first subcutaneous dose instead of next scheduled intravenous dose.

Intravenous Use for pJIA in Pediatric Patients ≥6 Years Old (2.2)

- Pediatric patients weighing <75 kg administer 10 mg/kg intravenously and those weighing ≥75 kg administer the adult intravenous dosing regimen (not to exceed a maximum dose of 1,000 mg), as a 30-minute infusion.
- Subsequently administer infusions at 2 and 4 weeks and every 4 weeks thereafter.

Subcutaneous Use for pJIA and PsA in Pediatric Patients ≥2 Years Old (2.2)

- Administer subcutaneously without an intravenous loading dose

Body Weight of Pediatric Patient | Dose (once weekly)
10 kg to less than 25 kg | 50 mg
25 kg to less than 50 kg | 87.5 mg
50 kg or more | 125 mg

Subcutaneous Use for Adult PsA (2.3)

- Administer 125 mg by subcutaneous injection once weekly without an intravenous loading dose.
- Patients switching from intravenous use to subcutaneous use, administer first subcutaneous dose instead of next scheduled intravenous dose.

Intravenous Use for Prophylaxis of aGVHD (2.4)

- For patients 6 years and older, administer at a 10 mg/kg dose (maximum dose 1,000 mg) as a 60-minute infusion on the day before transplantation, followed by a dose on Day 5, 14, and 28 after transplant.
- For patients 2 to less than 6 years old, administer a 15 mg/kg dose as a 60-minute infusion on the day before transplantation, followed by a 12 mg/kg dose as a 60-minute infusion on Day 5, 14, and 28 after transplant.

Preparation and Administration Instructions (2.5, 2.6)

- Administer as a 30-minute intravenous infusion for RA, pJIA, and adult PsA. (2.5)
- Administer as a 60-minute intravenous infusion for aGVHD prophylaxis. (2.5)
- See the Full Prescribing Information for preparation and administration instructions for intravenous infusion and recommendations for subcutaneous use. (2.5, 2.6) Prepare ORENCIA using only the silicone-free disposable syringe. (2.5)

3 DOSAGE FORMS AND STRENGTHS

Intravenous Infusion

- For injection: 250 mg lyophilized powder in a single-dose vial. (3)

Subcutaneous Use

- Injection: 50 mg/0.4 mL, 87.5 mg/0.7 mL, 125 mg/mL solution in single-dose prefilled syringe. (3)
- Injection: 125 mg/mL solution in a single-dose prefilled ClickJect™ autoinjectors. (3)

4 CONTRAINDICATIONS

None. (4)

5 WARNINGS AND PRECAUTIONS

- Concomitant use with a TNF antagonist can increase the risk of infections and serious infections. (5.1)
- Hypersensitivity and anaphylaxis have occurred. (5.2)
- Serious infections reported. Patients with a history of recurrent infections or underlying conditions predisposing to infections may experience more infections. Discontinue if a serious infection develops. (5.3)
- Screen for latent TB infection prior to initiating therapy. Patients testing positive should be treated prior to initiating ORENCIA. (5.3)
- Screen for viral hepatitis prior to initiating ORENCIA. (5.3)
- Update vaccinations prior to initiating ORENCIA. Live vaccines should not be given concurrently or within 3 months of discontinuation. ORENCIA may blunt the effectiveness of some immunizations. (5.4)
- COPD patients may develop more frequent respiratory adverse reactions. (5.5)
- Cytomegalovirus (CMV) and Epstein-Barr Virus (EBV) reactivation in patients treated for aGVHD prophylaxis. (5.7)

6 ADVERSE REACTIONS

- Most common adverse events (≥10%) in RA are headache, upper respiratory tract infection, nasopharyngitis, and nausea. (6.1)
- Most common adverse reactions (≥10%) in prophylaxis of aGVHD are anemia, hypertension, CMV reactivation/CMV infection, pyrexia, pneumonia, epistaxis, CD4 lymphocytes decreased, hypermagnesemia, and acute kidney injury. (6.1)

To report SUSPECTED ADVERSE REACTIONS, contact Bristol-Myers Squibb at 1-800-721-5072 or FDA at 1-800-FDA-1088 or www.fda.gov/medwatch.

FULL PRESCRIBING INFORMATION

1 INDICATIONS AND USAGE

1.1 Adult Rheumatoid Arthritis

ORENCIA® is indicated for the treatment of adult patients with moderately to severely active rheumatoid arthritis (RA).

1.2 Polyarticular Juvenile Idiopathic Arthritis

ORENCIA is indicated for the treatment of patients 2 years of age and older with moderately to severely active polyarticular juvenile idiopathic arthritis (pJIA).

1.3 Psoriatic Arthritis

ORENCIA is indicated for the treatment of patients 2 years of age and older with active psoriatic arthritis (PsA).

1.4 Prophylaxis for Acute Graft versus Host Disease

ORENCIA is indicated for the prophylaxis of acute graft versus host disease (aGVHD), in combination with a calcineurin inhibitor and methotrexate, in adults and pediatric patients 2 years of age and older undergoing hematopoietic stem cell transplantation (HSCT) from a matched or 1 allele-mismatched unrelated-donor.

1.5 Limitations of Use

The concomitant use of ORENCIA with other potent immunosuppressants [e.g., biologic disease-modifying antirheumatic drugs (bDMARDs), Janus kinase (JAK) inhibitors] is not recommended.

2 DOSAGE AND ADMINISTRATION

2.1 Dosage in Adult Rheumatoid Arthritis

For adult patients with RA, administer as an intravenous infusion or as a subcutaneous injection. ORENCIA may be used as monotherapy or concomitantly with disease-modifying antirheumatic drugs (DMARDs) other than JAK inhibitors or bDMARDs (e.g., TNF antagonists).

Intravenous Dosage

Reconstitute ORENCIA lyophilized powder and administer after dilution [see Dosage and Administration (2.5)] as a 30-minute intravenous infusion utilizing the weight range-based dosing recommended in Table 1. Following the initial intravenous infusion, administer as an intravenous infusion at 2 and 4 weeks and every 4 weeks thereafter.

Table 1: Dose of ORENCIA for Intravenous Infusion in Adult RA Patients
Body Weight of Adult Patient | Dose | Number of Vialsa
Less than 60 kg | 500 mg | 2
60 to 100 kg | 750 mg | 3
More than 100 kg | 1,000 mg | 4
a Each vial provides 250 mg of abatacept for administration.

Subcutaneous Dosage

Prior to the first subcutaneous dose, an optional loading dose may be administered as a single intravenous infusion (as per body weight categories in Table 1). If an intravenous loading dose is used, administer the first subcutaneous injection within one day of the infusion. Administer ORENCIA 125 mg in prefilled syringes or in ORENCIA ClickJect™ autoinjector by subcutaneous injection once weekly [see Dosage and Administration (2.6)].

For patients switching from ORENCIA intravenous therapy to subcutaneous administration, administer the first subcutaneous dose instead of the next scheduled intravenous dose.

2.2 Dosage in Polyarticular Juvenile Idiopathic Arthritis

For pediatric patients with pJIA, either administer ORENCIA as an intravenous infusion (only patients 6 years of age and older) or as a subcutaneous injection (only patients 2 years of age and older) [see Use in Specific Populations (8.4)]. ORENCIA may be used as monotherapy or concomitantly with methotrexate.

Intravenous Dosage

Administer ORENCIA as a 30-minute intravenous infusion based on body weight [see Dosage and Administration (2.5)]:

- For body weight less than 75 kg, administer a dose of 10 mg/kg.
- For body weight of 75 kg or greater, administer as per the recommendations in Table 1 (follow the adult intravenous dosing regimen), not to exceed a maximum dose of 1,000 mg.

Following the initial intravenous infusion, administer infusions at 2 and 4 weeks and every 4 weeks thereafter. Immediately discard any unused portion in the vials.

Subcutaneous Dosage

Administer ORENCIA for subcutaneous injection, without an intravenous loading dose, utilizing the weight range-based dosing as recommended in Table 2 [see Dosage and Administration (2.6)]. Subsequently administer once weekly.

Table 2: Dose of ORENCIA for Subcutaneous Administration in Patients 2 Years of Age and Older with pJIA
Body Weight of Pediatric Patient | Dose (once weekly)
10 to less than 25 kg | 50 mg
25 to less than 50 kg | 87.5 mg
50 kg or more | 125 mg

Patients with pJIA may self-inject with ORENCIA or the patient’s caregiver may administer ORENCIA if both the healthcare practitioner and the parent/legal guardian determine it is appropriate. The ability of pediatric patients to self-inject with the autoinjector has not been tested.

2.3 Dosage in Psoriatic Arthritis

Adult Patients

For adult patients with psoriatic arthritis, administer as an intravenous infusion or a subcutaneous injection.

ORENCIA may be used with or without non-biologic DMARDs.

Intravenous Dosage

Administer ORENCIA as a 30-minute intravenous infusion utilizing the weight range-based dosing specified in Table 1. Following the initial intravenous administration, administer an intravenous infusion at 2 and 4 weeks and every 4 weeks thereafter.

Subcutaneous Dosage

Administer 125 mg of ORENCIA subcutaneously once weekly (no intravenous loading dose is needed) [see Dosage and Administration (2.6)].

For patients switching from ORENCIA intravenous infusions to subcutaneous administration, administer the first subcutaneous dose instead of the next scheduled intravenous dose.

Pediatric Patients

Administer ORENCIA as a subcutaneous injection in pediatric patients 2 years of age and older with psoriatic arthritis [see Use in Specific Populations (8.4)]. ORENCIA may be used as monotherapy or concomitantly with methotrexate. Intravenous administration is not approved for pediatric patients with psoriatic arthritis.

Subcutaneous Dosage

Administer ORENCIA for subcutaneous injection weekly, utilizing the weight range-based dosage as recommended in Table 3 [see Dosage and Administration (2.6)].

Table 3: Dose of ORENCIA for Subcutaneous Administration in Patients 2 Years of Age and Older with Psoriatic Arthritis
Body Weight of Pediatric Patient | Dose (once weekly)
10 to less than 25 kg | 50 mg
25 to less than 50 kg | 87.5 mg
50 kg or more | 125 mg

Pediatric patients with psoriatic arthritis may self-inject with ORENCIA or the patient’s caregiver may administer ORENCIA if both the healthcare practitioner and the parent/legal guardian determine it is appropriate. The ability of pediatric patients to self-inject with the autoinjector has not been tested.

2.4 Dosage in Prophylaxis of Acute Graft versus Host Disease in Adults and Pediatric Patients Aged 2 Years and Older

Antiviral Prophylactic Treatment

Before administering ORENCIA, administer recommended antiviral prophylactic treatment for Epstein-Barr Virus (EBV) reactivation, and continue for six months following HSCT. In addition, consider prophylactic antivirals for Cytomegalovirus (CMV) infection/reactivation during treatment and for six months following HSCT [see Warnings and Precautions (5.7)].

Intravenous Dosing Regimen

For patients 6 years and older, administer ORENCIA 10 mg/kg (maximum dose of 1,000 mg) as an intravenous infusion over 60 minutes on the day before transplantation (Day -1), followed by administration on Days 5, 14, and 28 after transplantation.

For patients 2 to less than 6 years old, administer ORENCIA 15 mg/kg as an intravenous infusion over 60 minutes on the day before transplantation (Day -1), followed by 12 mg/kg as an intravenous infusion over 60 minutes on Days 5, 14, and 28 after transplantation.

2.5 Preparation and Administration Instructions for Intravenous Infusion

Calculate the ORENCIA dose, the total volume of reconstituted solution required, and the number of ORENCIA vials needed. For a full dose, less than the full contents of one vial or more than one vial may be needed. Using aseptic technique, reconstitute, dilute, and then administer ORENCIA as follows:

Reconstitution

1) Use the vial only if the vacuum is present.
2) Reconstitute each vial of supplied ORENCIA lyophilized powder (each vial supplies 250 mg of abatacept) with 10 mL of Sterile Water for Injection, USP (direct the stream toward the inside wall of the vial) to obtain a concentration of 25 mg/mL. Use only the provided silicone-free syringe with an 18- to 21-gauge needle:
  a. If the ORENCIA lyophilized powder is accidently reconstituted using a siliconized syringe, the solution may develop a few translucent particles (discard any solutions prepared using siliconized syringes).
  b. If the silicone-free disposable syringe is dropped or becomes contaminated, use a new silicone-free disposable syringe. To obtain new silicone-free syringes, contact Bristol-Myers Squibb at 1-800-ORENCIA.
3) Gently swirl the vial to minimize foam formation, until the contents are completely dissolved. Do not shake. Avoid prolonged or vigorous agitation.
4) Upon complete dissolution of the lyophilized powder, vent the vial with a needle to dissipate any foam that may be present.
5) Visually inspect the reconstituted solution (the solution should be clear and colorless to pale yellow). Do not use if opaque particles, discoloration, or other foreign particles are present.
6) Repeat steps 2) through 5) if two, three, or four vials are needed for a dose (see Table 1).

Dilution

7) Must further dilute the reconstituted ORENCIA solution to 100 mL as follows:
  a. From a 100 mL infusion bag or bottle of 0.9% Sodium Chloride Injection, USP, withdraw a volume equal to the volume of the reconstituted ORENCIA solution required for the patient’s dose.
  b. Slowly add the reconstituted ORENCIA solution(s) into the infusion bag or bottle using the silicone-free disposable syringe provided with each vial.
  c. Gently mix. Do not shake the bag or bottle. The final concentration of abatacept in the bag or bottle will depend upon the amount of abatacept added, but will be no more than 10 mg/mL. Immediately discard any unused portion in the ORENCIA vial.

Administration

8) Prior to administration, visually inspect the ORENCIA diluted solution for particulate matter and discoloration. Discard the diluted solution if any particulate matter or discoloration is observed.
9) Using an infusion set and a sterile, non-pyrogenic, low-protein-binding filter (pore size of 0.2 μm to 1.2 μm), administer the entire diluted ORENCIA solution over:
3. 30 minutes for RA, pJIA, and adults with PsA
4. 60 minutes for aGVHD prophylaxis
10) Must complete the infusion of the diluted ORENCIA solution within 24 hours of reconstitution of the ORENCIA vials.

Do not infuse ORENCIA concomitantly in the same intravenous line with other agents. No physical or biochemical compatibility studies have been conducted to evaluate the coadministration of ORENCIA with other drugs.

Storage of Diluted ORENCIA Solution

May store the diluted ORENCIA solution at room temperature or refrigerate at 2ºC to 8ºC (36ºF to 46ºF) up to 24 hours before use. Discard the diluted solution if not administered within 24 hours.

2.6 Recommendations for Subcutaneous Administration

ORENCIA prefilled syringes and ORENCIA ClickJect autoinjectors are intended for:

- Subcutaneous use only and are not intended for intravenous infusion.
- Use under the guidance of a healthcare practitioner.

After proper training in subcutaneous injection technique, a patient or the patient’s caregiver may administer a subcutaneous injection of ORENCIA (ClickJect autoinjector or prefilled syringe) if a healthcare practitioner determines that it is appropriate. Instruct patients and/or caregivers to follow the directions provided in the Instructions for Use for additional details on administration. Specifically instruct them to inject the full amount (which provides the proper dose of ORENCIA), rotate injection sites, and to avoid injections into areas where the skin is tender, bruised, red, or hard.

Visually inspect for particulate matter and discoloration prior to administration. Do not use ORENCIA prefilled syringes or ORENCIA ClickJect autoinjectors exhibiting particulate matter or discoloration. ORENCIA should be clear to slightly opalescent and colorless to pale yellow.

3 DOSAGE FORMS AND STRENGTHS

DOSAGE FORMS AND STRENGTHS

- Intravenous Infusion
For injection: 250 mg white lyophilized powder in a single-dose vial [see Dosage and Administration (2.1, 2.2, 2.3, 2.5)].
- Subcutaneous Use
Injection: 50 mg/0.4 mL, 87.5 mg/0.7 mL, and 125 mg/mL of a clear to slightly opalescent, colorless to pale-yellow solution in a single-dose prefilled glass syringe.
Injection: 125 mg/mL of a clear to slightly opalescent, colorless to pale-yellow solution in a single-dose prefilled ClickJect autoinjector.

4 CONTRAINDICATIONS

None.

5 WARNINGS AND PRECAUTIONS

5.1 Increased Risk of Infection with Concomitant Use of TNF Antagonists, Other Biologic RA/PsA Therapy, or JAK Inhibitors

In controlled clinical trials in patients with adult RA, patients receiving concomitant intravenous ORENCIA and TNF antagonist therapy experienced more infections (63% vs. 43%) and serious infections (4.4% vs. 0.8%) compared to patients treated with only TNF antagonists [see Adverse Reactions (6.1)]. These trials failed to demonstrate an important enhancement of efficacy with concomitant administration of ORENCIA with TNF antagonists; therefore, concurrent therapy with ORENCIA and a TNF antagonist is not recommended. While transitioning from TNF antagonist therapy to ORENCIA therapy, patients should be monitored for signs of infection. Additionally, concomitant use of ORENCIA with other biologic RA/PsA therapy or JAK inhibitors is not recommended.

5.2 Hypersensitivity Reactions

In clinical trials of 2688 adult RA patients treated with intravenous ORENCIA, there were two cases (<0.1%) of anaphylaxis reactions. Other reactions potentially associated with drug hypersensitivity, such as hypotension, urticaria, and dyspnea, each occurred in less than 0.9% of ORENCIA-treated patients. Of the 190 ORENCIA-treated patients in pJIA clinical trials, there was one case of a hypersensitivity reaction (0.5%) [see Adverse Reactions (6.1)].

In postmarketing experience, fatal anaphylaxis following the first infusion of ORENCIA and life-threatening cases of angioedema have been reported. Angioedema has occurred as early as after the first dose of ORENCIA, but also has occurred with subsequent doses. Angioedema reactions have occurred within hours of administration and in some instances had a delayed onset (i.e., days).

Appropriate medical support measures for the treatment of hypersensitivity reactions should be available for immediate use in the event of a reaction. If an anaphylactic or other serious allergic reaction occurs, administration of intravenous or subcutaneous ORENCIA should be stopped immediately with appropriate therapy instituted, and the use of ORENCIA should be permanently discontinued.

5.3 Infections

Serious infections, including sepsis and pneumonia, have been reported in patients receiving ORENCIA (serious infections were reported in 3% and 1.9% of RA patients treated with intravenous ORENCIA and placebo, respectively) [see Adverse Reactions (6.1)]. Some of these infections have been fatal. Many of the serious infections have occurred in patients on concomitant immunosuppressive therapy which in addition to their underlying disease, could further predispose them to infection. A higher rate of serious infections has been observed in adult RA patients treated with concurrent TNF antagonists and ORENCIA compared to those treated with ORENCIA alone [see Warnings and Precautions (5.1)].

Healthcare providers should exercise caution when considering the use of ORENCIA in patients with a history of recurrent infections, underlying conditions which may predispose them to infections, or chronic, latent, or localized infections. Patients who develop a new infection while undergoing treatment with ORENCIA should be monitored closely. Administration of ORENCIA should be discontinued if a patient develops a serious infection.

Prior to initiating ORENCIA, patients should be screened for latent tuberculosis (TB) infection according to current TB guidelines. ORENCIA has not been studied in patients with a positive TB screen, and the safety of ORENCIA in individuals with latent TB infection is unknown. Patients testing positive in TB screening should be treated by standard medical practice prior to therapy with ORENCIA.

Antirheumatic therapies have been associated with hepatitis B reactivation. Therefore, screening for viral hepatitis should be performed in accordance with published guidelines before starting therapy with ORENCIA. In clinical studies with ORENCIA, patients who screened positive for hepatitis were excluded from study.

5.4 Immunizations

Prior to initiating ORENCIA in pediatric and adult patients, update vaccinations in accordance with current vaccination guidelines. ORENCIA-treated patients may receive current non-live vaccines. Live vaccines should not be given concurrently with ORENCIA or within 3 months after discontinuation. No data are available on the secondary transmission of infection from persons receiving live vaccines to patients receiving ORENCIA. In addition, there are clinical considerations for administering live vaccines to infants who were exposed to ORENCIA while in utero [see Use in Specific Populations (8.1)]. Based on its mechanism of action, ORENCIA may blunt the effectiveness of some immunizations.

5.5 Increased Risk of Adverse Reactions When Used in Patients with Chronic Obstructive Pulmonary Disease (COPD)

In Study V, adult COPD patients treated with ORENCIA for RA developed adverse reactions more frequently than those treated with placebo, including COPD exacerbations, cough, rhonchi, and dyspnea. A greater percentage of patients treated with ORENCIA developed a serious adverse event compared to patients treated with placebo (27% vs 6%) [see Clinical Studies (14.1) and Adverse Reactions (6.1)]. Use of ORENCIA in patients with COPD should be undertaken with caution and such patients should be monitored for worsening of their respiratory status.

5.6 Immunosuppression

The possibility exists for drugs inhibiting T-cell activation, including ORENCIA, to affect host defenses against infections and malignancies since T cells mediate cellular immune responses. In clinical trials in patients with adult RA, a higher rate of infections was seen in ORENCIA-treated patients compared to placebo-treated patients [see Warnings and Precautions (5.3) and Adverse Reactions (6.1)]. The impact of treatment with ORENCIA on the development and course of malignancies is not fully understood [see Adverse Reactions (6.1)]. There have been reports of malignancies, including skin cancer in patients receiving ORENCIA [see Adverse Reactions (6.3)]. Periodic skin examinations are recommended for all ORENCIA-treated patients, particularly those with risk factors for skin cancer.

5.7 Cytomegalovirus (CMV) and Epstein-Barr Virus (EBV) Reactivation in aGVHD Prophylaxis after Hematopoietic Stem Cell Transplant (HSCT)

Post-Transplant Lymphoproliferative Disorder (PTLD) occurred in patients who received ORENCIA for aGVHD prophylaxis during unrelated HSCT. Of 116 patients who received ORENCIA, 4 patients (3.4%) experienced PTLD. All the PTLD events were associated with Epstein-Barr virus (EBV) infection. Three of the four patients were EBV serology positive at baseline; one patient had negative baseline EBV serology with donor EBV serology unknown. Three of the 4 patients discontinued acyclovir prophylaxis at day 30 post-transplant. The range of time to onset of the events was 49 to 89 days post-transplant. Monitor patients for EBV reactivation in accordance with institutional practices. Provide prophylaxis for EBV infection for 6 months post-transplantation to prevent EBV-associated PTLD [see Dosage and Administration (2.4)].

Cytomegalovirus (CMV) invasive disease occurred in patients who received ORENCIA for aGVHD prophylaxis during unrelated HSCT. Of 116 patients who received ORENCIA, 7% experienced CMV invasive diseases up to day 225 post-transplant. All the patients who experienced CMV invasive disease were CMV serology positive at baseline. The median time to onset of the event was 91 days post-transplant. CMV invasive diseases predominantly involved the gastrointestinal tract [see Adverse Reactions (6.1)].

Monitor patients for CMV infection/reactivation for 6 months post-transplant regardless of the results of donor and recipient pre-transplant CMV serology. Consider prophylaxis for CMV infection/reactivation [see Dosage and Administration (2.4)].

6 ADVERSE REACTIONS

The following clinically significant adverse reactions are described elsewhere in the labeling:

- Increased Risk of Infection with Concomitant Use with TNF Antagonists, Other Biologic RA/PsA Therapy, or JAK Inhibitors [see Warnings and Precautions (5.1)]
- Hypersensitivity Reactions [see Warnings and Precautions (5.2)]
- Infections [see Warnings and Precautions (5.3)]
- Increased Risk of Adverse Reactions When Used in Patients with Chronic Obstructive Pulmonary Disease (COPD) [see Warnings and Precautions (5.5)]
- Immunosuppression [see Warnings and Precautions (5.6)]
- Cytomegalovirus (CMV) and Epstein-Barr Virus (EBV) Reactivation in aGVHD Prophylaxis after Hematopoietic Stem Cell Transplant (HSCT) [see Warnings and Precautions (5.7)]

6.1 Clinical Trials Experience

Because clinical trials are conducted under widely varying and controlled conditions, adverse reaction rates observed in clinical trials of a drug cannot be directly compared to rates in the clinical trials of another drug and may not predict the rates observed in a broader patient population in clinical practice.

Adverse Reactions in Adult Patients with RA Treated with Intravenous ORENCIA

The data from placebo-controlled studies described herein reflect exposure to ORENCIA administered intravenously in patients with active RA (1955 patients with ORENCIA, 989 with placebo) (Studies I through VI) [see Clinical Studies (14.1)]. The studies had either a double-blind, placebo-controlled period of 6 months (258 patients with ORENCIA, 133 with placebo) or 1 year (1697 patients with ORENCIA, 856 with placebo). A subset of these patients received concomitant biologic DMARD therapy, such as a TNF antagonist (204 patients with ORENCIA, 134 with placebo). The concomitant use of ORENCIA with a TNF antagonist is not recommended [see Indications and Usage (1.5)]. The majority of patients in RA clinical studies received one or more of the following concomitant medications with ORENCIA: methotrexate, nonsteroidal anti-inflammatory drugs (NSAIDs), corticosteroids, TNF antagonist, azathioprine, chloroquine, gold, hydroxychloroquine, leflunomide, sulfasalazine, and anakinra.

The most serious adverse reactions were serious infections and malignancies. The most commonly reported adverse events (occurring in ≥10% of patients treated with ORENCIA) were headache, upper respiratory tract infection, nasopharyngitis, and nausea.

The adverse reactions most frequently resulting in clinical intervention (interruption or discontinuation of ORENCIA) were due to infection. The most frequently reported infections resulting in dose interruption were upper respiratory tract infection (1%), bronchitis (0.7%), and herpes zoster (0.7%). The most frequent infections resulting in discontinuation were pneumonia (0.2%), localized infection (0.2%), and bronchitis (0.1%).

Most Common Adverse Reactions in Adult Patients with RA Treated with Intravenous ORENCIA

Adverse reactions occurring in 3% or more of patients and at least 1% more frequently in ORENCIA-treated patients (intravenous) during placebo-controlled RA studies are summarized in Table 4.

Table 4: Most Common Adverse Reactions* During Placebo-Controlled RA Studies of Intravenous ORENCIA
 | Intravenous ORENCIA (n=1955)a | Placebo (n=989)b
Headache | 18% | 13%
Nasopharyngitis | 12% | 9%
Dizziness | 9% | 7%
Cough | 8% | 7%
Back pain | 7% | 6%
Hypertension | 7% | 4%
Dyspepsia | 6% | 4%
Urinary tract infection | 6% | 5%
Rash | 4% | 3%
Pain in extremity | 3% | 2%
* Occurred in ≥3% patients and >1% more frequently in ORENCIA-treated patients.
a Includes 204 patients on concomitant biologic DMARDs (adalimumab, anakinra, etanercept, or infliximab).
b Includes 134 patients on concomitant biologic DMARDs (adalimumab, anakinra, etanercept, or infliximab).

Infections in Adult Patients with RA Treated with Intravenous ORENCIA

In the placebo-controlled trials in patients with RA, infections were reported in 54% of intravenous ORENCIA-treated patients and 48% of placebo-treated patients. The most commonly reported infections (reported in 5%-13% of patients) were upper respiratory tract infection, nasopharyngitis, sinusitis, urinary tract infection, influenza, and bronchitis. Other infections reported in fewer than 5% of patients at a higher frequency (>0.5%) with ORENCIA compared to placebo, were rhinitis, herpes simplex, and pneumonia [see Warnings and Precautions (5.3)].

Serious infections were reported in 3% of patients treated with ORENCIA and 1.9% of patients treated with placebo. The most common (0.2%-0.5%) serious infections reported with ORENCIA were pneumonia, cellulitis, urinary tract infection, bronchitis, diverticulitis, and acute pyelonephritis [see Warnings and Precautions (5.3)].

Malignancies in Adult Patients with RA Treated with Intravenous ORENCIA

In the placebo-controlled portions of the clinical trials (1955 patients treated for RA with ORENCIA for a median of 12 months), the overall frequencies of malignancies were similar in the ORENCIA- and placebo-treated patients (1.3% and 1.1%, respectively). However, more cases of lung cancer were observed in ORENCIA-treated patients (4 cases, 0.2%) than placebo-treated patients (0 cases, 0%). In the cumulative intravenous ORENCIA clinical trials in patients with RA (placebo-controlled and uncontrolled, open-label) a total of 8 cases of lung cancer (0.21 cases per 100 patient-years) and 4 lymphomas (0.10 cases per 100 patient-years) were observed in 2688 patients (3827 patient-years). The rate observed for lymphoma is approximately 3.5-fold higher than expected in an age- and gender-matched general population based on the National Cancer Institute's Surveillance, Epidemiology, and End Results Database. Patients with RA, particularly those with highly active disease, are at a higher risk for the development of lymphoma. Other malignancies included skin, breast, bile duct, bladder, cervical, endometrial, lymphoma, melanoma, myelodysplastic syndrome, ovarian, prostate, renal, thyroid, and uterine cancers [see Warnings and Precautions (5.6)]. The potential role of ORENCIA in the development of malignancies in humans is unknown.

Infusion-Related Reactions and Hypersensitivity Reactions in Adult Patients with RA Treated with Intravenous ORENCIA

Acute infusion-related events (adverse reactions occurring within 1 hour of the start of the infusion) in Studies III, IV, and V [see Clinical Studies (14.1)] were more common in the ORENCIA-treated patients than the placebo patients (9% for ORENCIA, 6% for placebo). The most frequently reported events (1%-2%) were dizziness, headache, and hypertension.

Acute infusion-related events that were reported in >0.1% and ≤1% of patients treated with ORENCIA included cardiopulmonary symptoms, such as hypotension, increased blood pressure, and dyspnea; other symptoms included nausea, flushing, urticaria, cough, hypersensitivity, pruritus, rash, and wheezing. Most of these reactions were mild (68%) to moderate (28%). Fewer than 1% of ORENCIA-treated patients discontinued due to an acute infusion-related event. In controlled trials, 6 ORENCIA-treated patients compared to 2 placebo-treated patients discontinued study treatment due to acute infusion-related events.

In clinical trials of 2688 adult RA patients treated with intravenous ORENCIA, there were two cases (<0.1%) of anaphylaxis. Other reactions potentially associated with drug hypersensitivity, such as hypotension, urticaria, and dyspnea, each occurred in less than 0.9% of ORENCIA-treated patients and generally occurred within 24 hours of ORENCIA infusion. Appropriate medical support measures for the treatment of hypersensitivity reactions should be available for immediate use in the event of a reaction [see Warnings and Precautions (5.2)].

Adverse Reactions in Patients with COPD Treated for RA with Intravenous ORENCIA

In Study V [see Clinical Studies (14.1)], there were 37 and 17 patients with chronic obstructive pulmonary disease (COPD) who were treated for RA with ORENCIA and placebo, respectively. The COPD patients treated with ORENCIA for RA developed adverse events more frequently than those treated with placebo (97% vs 88%, respectively). Respiratory disorders occurred more frequently in ORENCIA-treated patients compared to placebo-treated patients (43% vs 24%, respectively) including COPD exacerbation, cough, rhonchi, and dyspnea. A greater percentage of ORENCIA-treated patients developed a serious adverse event compared to placebo-treated patients (27% vs 6%), including COPD exacerbation [3 of 37 patients (8%)] and pneumonia [1 of 37 patients (3%)] [see Warnings and Precautions (5.5)].

Adverse Reactions in Methotrexate-Naive Patients with RA Treated with Intravenous ORENCIA

Study VI was an active-controlled clinical trial in methotrexate-naive patients [see Clinical Studies (14.1)]. The safety experience in these patients was consistent with the patients in Studies I-V.

Adverse Reactions in Adult Patients with RA Treated with Subcutaneous or Intravenous ORENCIA

The data described below are derived from Study SC-1. Study SC-1 was a randomized, double-blind, double-dummy, non-inferiority study that compared the safety of ORENCIA administered subcutaneously or intravenously in 1457 patients with RA, who received background methotrexate, and experienced an inadequate response to methotrexate (MTX-IR) [see Clinical Studies (14.1)]. The adverse reaction profile in patients treated with subcutaneous ORENCIA was similar to the adverse reaction profile in patients treated with intravenous ORENCIA and consistent with intravenous ORENCIA administered in Studies I-VI.

Injection Site Reactions in Adult RA Patients Treated with Subcutaneous ORENCIA

The overall frequency of injection site reactions in Study SC-1 was 2.6% (19/736) and 2.5% (18/721) for the subcutaneous ORENCIA group and the subcutaneous placebo group (given intravenous ORENCIA), respectively [see Clinical Studies (14.1)]. All these injection site reactions (including hematoma, pruritus, and erythema) were mild (83%) to moderate (17%) in severity, and none necessitated drug discontinuation.

Adverse Reactions in Adult Patients with PsA Treated with Intravenous or Subcutaneous ORENCIA

The safety of ORENCIA was evaluated in 594 patients with PsA (341 patients on ORENCIA and 253 patients on placebo), in two randomized, double-blind, placebo-controlled trials [see Clinical Studies (14.3)]. Of the 341 patients who received ORENCIA, 128 patients received intravenous ORENCIA (PsA-I) and 213 patients received subcutaneous ORENCIA (PsA-II). The safety profile was comparable between ORENCIA given intravenously in Study PsA-I and ORENCIA given subcutaneously in Study PsA-II and also consistent with the safety profile of ORENCIA in patients with RA [see Warnings and Precautions (5), Adverse Reactions (6.1)].

Adverse Reactions in Patients with pJIA Treated with Intravenous ORENCIA

In general, the adverse events in pediatric patients with polyarticular JIA (pJIA) treated with intravenous ORENCIA were similar in frequency and type to those seen in adult patients with RA treated with intravenous ORENCIA [see Warnings and Precautions (5) and Adverse Reactions (6)].

Study JIA-1 was a three-part study including an open-label extension that assessed the safety of intravenous ORENCIA in 190 pediatric patients, 6 to 17 years of age, with pJIA. Overall frequency of adverse events in the 4‑month, lead-in, open-label period of the study was 70%; infections occurred at a frequency of 36% [see Clinical Studies (14.2)]. The most common infections were upper respiratory tract infection and nasopharyngitis. The infections resolved without sequelae, and the types of infections were consistent with those commonly seen in outpatient pediatric populations. Other events that occurred at a prevalence of at least 5% were headache, nausea, diarrhea, cough, pyrexia, and abdominal pain.

A total of 6 serious adverse events [acute lymphocytic leukemia, ovarian cyst, varicella infection, disease flare (2), and joint wear] were reported during the initial 4 months of treatment with intravenous ORENCIA.

Of the 190 pediatric patients with pJIA treated with intravenous ORENCIA in clinical trials, there was one case of a hypersensitivity reaction (0.5%). During Periods A, B, and C, acute infusion-related reactions occurred at a frequency of 4%, 2%, and 3%, respectively, and were consistent with the types of events reported in adults.

Upon continued treatment in the open-label extension period, the types of adverse events were similar in frequency and type to those seen in adult patients, except for a single patient diagnosed with multiple sclerosis while on open-label treatment.

Adverse Reactions in Patients with pJIA Treated with Subcutaneous ORENCIA

Study JIA-2 was an open-label study with a 4-month short-term period and a long-term extension period that assessed the safety of subcutaneous ORENCIA in 205 pediatric patients, 2 to 17 years of age with pJIA. The adverse reaction profile in patients with pJIA treated with ORENCIA administered subcutaneously in Study JIA-2 were consistent with the adverse reaction profile in patients with pJIA treated with intravenous Study JIA-1.

There were no reported cases of hypersensitivity reactions. Local injection‑site reactions occurred at a frequency of 4.4%.

Adverse Reactions in Patients Undergoing Unrelated-Donor Hematopoietic Stem Cell Transplantation (HSCT) with Intravenous ORENCIA

The data described herein were from one clinical study of ORENCIA (GVHD-1) for aGVHD prophylaxis in patients 6 years and older with hematologic malignancies who were undergoing unrelated HSCT wherein all patients were receiving calcineurin inhibitor and methotrexate as the standard of care for aGVHD prophylaxis [see Clinical Studies (14.4)]. Two cohorts were studied at 10 mg/kg (maximum dose of 1,000 mg) as an intravenous infusion over 60 minutes on the day before transplantation (Day-1), followed by administration on Days 5, 14, and 28 after transplantation:

1) A single-arm cohort of ORENCIA-treated patients (n=43) who underwent 7 of 8 Human leukocyte antigen (HLA)-matched HSCT from unrelated donors (7 of 8 cohort) and

2) A randomized cohort comprised of ORENCIA-treated patients (n=73) and placebo-treated patients (n=69) who underwent 8 of 8 HLA-matched HSCT from unrelated donors (8 of 8 cohort).

Of the 116 patients who received ORENCIA, 27 (23%) were 6 to less than 17 years of age [see Use in Specific Populations (8.4)].

The safety information from the date of first dose of ORENCIA up to Day 225 post-transplantation from this study is presented below. The incidence of adverse reactions was determined based on pooled data of ORENCIA-treated patients from the 2 study cohorts (n=116).

Serious adverse reactions reported in > 5% of patients who received ORENCIA in combination with a calcineurin inhibitor and methotrexate included pyrexia (20%), pneumonia (8%), acute kidney injury (7%), diarrhea (6%), hypoxia (5%), and nausea (5%).

Permanent discontinuation of ORENCIA due to an adverse reaction occurred in two patients (1.7%) due to one case each of pneumonia and allergic reaction.

The most common (≥10%) adverse reactions in the ORENCIA treated patients were anemia, hypertension, CMV reactivation/CMV infection, pyrexia, pneumonia, epistaxis, CD4 lymphocytes decreased, hypermagnesemia, and acute kidney injury.

Table 5 summarizes the frequency of adverse reactions reported in the study of ORENCIA in GVHD-1.

Table 5: Adverse Reactions (≥10%) in Patients with aGVHD Who Received ORENCIA with a Difference Between Arms of >2% Compared to Placebo in GVHD-1
 | 7 of 8 Cohort |  | 8 of 8 Cohort
Adverse Reaction | ORENCIA (+CNI and MTX) (N=43) |  | ORENCIA (+CNI and MTX) (N=73) |  | Placebo (+CNI and MTX) (N=69)
 | All Grades; (%) | Grade 3 or 4; (%) | All Grades; (%) | Grade 3 or 4; (%) | All Grades; (%) | Grade 3 or 4; (%)
Blood and Lymphatic System Disorders
Anemia | 56 | 56 | 69 | 69 | 57 | 57
CD4 lymphocytes decreased | 14 | 14 | 14 | 14 | 9 | 9
Vascular Disorders
Hypertension | 49 | 49 | 43 | 43 | 38 | 38
General Disorders and Administrative Site Conditions
Pyrexia | 28 | 9 | 19 | 10 | 20 | 4
Infections and Infestations
CMV Reactivation/CMV Infection | 26 | 26 | 32 | 32 | 22 | 22
Pneumonia | 19 | 19 | 12 | 12 | 10 | 9
Respiratory and Mediastinal Disorders
Epistaxis | 12 | 12 | 16 | 16 | 10 | 10
Renal and Urinary Disorders
Acute kidney injury | 9 | 7 | 15 | 15 | 10 | 10
Metabolism and Nutrition Disorders
Hypermagnesemia | 5 | 5 | 18 | 18 | 10 | 10

Clinically relevant adverse reactions in <10% of patients who received ORENCIA in combination with calcineurin inhibitor and methotrexate in Study GVHD-1 included EBV reactivation.

6.2 Immunogenicity

As with all therapeutic proteins, there is potential for immunogenicity. The detection of antibody formation is highly dependent on the sensitivity and specificity of the assay. Additionally, the observed incidence of antibody (including neutralizing antibody) positivity in an assay may be influenced by several factors, including assay methodology, sample handling, timing of sample collection, concomitant medications, and underlying disease. For these reasons, comparison of the incidence of antibodies in the studies described below with the incidence of antibodies in other studies or to other abatacept products may be misleading.

Immunogenicity in Adult Patients with RA Treated with Intravenous ORENCIA

Antibodies directed against the entire abatacept molecule or to the CTLA-4 portion of abatacept were assessed by ELISA assays in RA patients for up to 2 years following repeated treatment with intravenous ORENCIA. Thirty-four of 1993 (2%) patients developed binding antibodies to the entire abatacept molecule or to the CTLA-4 portion of abatacept. Because trough levels of abatacept can interfere with assay results, a subset analysis was performed. In the subset analysis, 9 of 154 (6%) patients that had discontinued intravenous ORENCIA treatment for over 56 days developed antibodies. Samples with confirmed binding activity to CTLA-4 were assessed for the presence of neutralizing antibodies in a cell-based luciferase reporter assay. Six of 9 (67%) evaluable patients were shown to possess neutralizing antibodies. However, the development of neutralizing antibodies may be underreported due to lack of assay sensitivity.

No correlation of anti-abatacept antibody development to clinical response or adverse events was observed.

Immunogenicity in Adult RA Patients Treated with Subcutaneous or Intravenous ORENCIA

Study SC-1 compared the immunogenicity to abatacept following subcutaneous or intravenous ORENCIA administration. The overall immunogenicity frequency to abatacept was 1% (8/725) and 2% (16/710) for the subcutaneous and intravenous groups, respectively. The rate is consistent with previous experience, and there was no correlation of immunogenicity with effects on pharmacokinetics, safety, or efficacy.

Immunogenicity in Adult RA Patients Treated with Subcutaneous ORENCIA Monotherapy

Study SC-2 was conducted to determine the effect of subcutaneous monotherapy use of ORENCIA on immunogenicity (without an intravenous loading dose) in 100 RA patients, who had not previously received ORENCIA or other CTLA4Ig. Patients in this study received either subcutaneous ORENCIA plus methotrexate (n=51) or subcutaneous ORENCIA monotherapy (n=49). No patients in either group developed anti-abatacept antibodies after 4 months of treatment. The safety observed in this study was consistent with that observed in the other subcutaneous studies.

Immunogenicity in Adult RA Patients After Treatment, Withdrawal, and then Restart of Subcutaneous ORENCIA

Study SC-3 was conducted to investigate the immunogenicity in adult RA patients after treatment, withdrawal (three months), and restart of ORENCIA subcutaneous treatment (patients were treated concomitantly with methotrexate). One hundred sixty-seven patients were enrolled in the first 3‑month treatment period and responders (n=120) were randomized to either subcutaneous ORENCIA or placebo for the second 3-month period (withdrawal period). Patients from this period then received open-label ORENCIA treatment in the final 3-month period of the study (period 3). At the end of the withdrawal period, 0/38 (0%) patients who continued to receive subcutaneous ORENCIA developed anti-abatacept antibodies compared to 7/73 (10%) of patients who had subcutaneous ORENCIA withdrawn during this period. Half of the patients who received subcutaneous placebo during the withdrawal period received a single intravenous infusion of ORENCIA at the start of period 3 and half received intravenous placebo. At the end of period 3, when all patients again received subcutaneous ORENCIA, the immunogenicity rates were 1/38 (3%) in the group who received subcutaneous ORENCIA throughout, and 2/73 (3%) in the group that had received placebo during the withdrawal period. Upon reinitiating therapy, there were no injection reactions and no differences in response to therapy in patients who were withdrawn from subcutaneous therapy for up to 3 months compared to those who remained on subcutaneous therapy (these results occurred in those who received or did not receive an intravenous loading dose). The safety observed in this study was consistent with that observed in the other studies.

Immunogenicity in Patients with pJIA Treated with Intravenous ORENCIA

Antibodies directed against the entire abatacept molecule or to the CTLA-4 portion of abatacept were assessed by ELISA assays in patients with pJIA following repeated treatment with intravenous ORENCIA throughout the open-label period. For patients who were withdrawn from therapy for up to 6 months during the double-blind period, the rate of antibody formation to the CTLA-4 portion of the molecule was 41% (22/54), while for those who remained on therapy the rate was 13% (7/54). Twenty of these patients had samples that could be tested for antibodies with neutralizing activity; of these, 8 (40%) patients were shown to possess neutralizing antibodies.

The presence of antibodies was generally transient, and titers were low. The presence of antibodies was not associated with adverse events, changes in efficacy, or an effect on serum concentrations of abatacept. For patients who were withdrawn from ORENCIA during the double-blind period for up to 6 months, no serious acute infusion-related events were observed upon re-initiation of ORENCIA therapy.

Immunogenicity in Patients Treated for Prophylaxis of aGVHD with Intravenous ORENCIA

Immunogenicity was assessed in patients undergoing HSCT. Overall, immunogenicity incidence and associated antibody titers were low from the 4-dose intravenous ORENCIA regimen used in this study. Of the 114 immunogenicity evaluable subjects in the ORENCIA groups, none were positive during the ORENCIA treatment period (Day -1 to Day 28 following transplant). During the off-treatment period (Day 29 and up to Day 180 following transplant); 6 of 91 immunogenicity evaluable subjects (6.6%) were positive for CTLA4 and possibly Ig; 4 of the 6 positive subjects were found to have at least one positive sample with neutralization activity. In this study, immunogenicity positive subjects only had ADA positive samples on Day 180 (off-treatment period) and thus due to the timing of the response, the impact on PK, safety, or efficacy could not be determined.

6.3 Postmarketing Experience

Adverse reactions have been reported during the postapproval use of ORENCIA. Because these reactions are reported voluntarily from a population of uncertain size, it is not always possible to reliably estimate their frequency or establish a causal relationship to ORENCIA. Based on the postmarketing experience with ORENCIA, the following adverse reactions have been identified:

- Vasculitis (including cutaneous vasculitis and leukocytoclastic vasculitis)
- New or worsening psoriasis
- Non-melanoma skin cancers (basal cell carcinoma and squamous cell carcinoma)
- Angioedema reactions [see Warnings and Precautions (5.2)]

During postmarketing experience with intravenous ORENCIA, systemic infusion reactions were similar to that seen in the clinical trial experience with intravenous ORENCIA with the exception of one case of fatal anaphylaxis [see Warnings and Precautions (5.2)]. Postmarketing reports of systemic injection reactions (e.g., pruritus, throat tightness, dyspnea) have occurred following the use of subcutaneous ORENCIA.

7 DRUG INTERACTIONS

7.1 Immunosuppressants

Concomitant administration of a TNF antagonist with ORENCIA has been associated with an increased risk of serious infections and no significant additional efficacy over use of the TNF antagonists alone. Concurrent therapy with ORENCIA and TNF antagonists is not recommended [see Warnings and Precautions (5.1)].

There is insufficient experience to assess the safety and efficacy of ORENCIA administered concurrently with other biologic RA therapy, such as anakinra, or other biologic PsA therapy, and JAK inhibitors and therefore such use is not recommended. [see Warnings and Precautions (5.1)].

7.2 Blood Glucose Testing

Parenteral drug products containing maltose can interfere with the readings of blood glucose monitors that use test strips with glucose dehydrogenase pyrroloquinoline quinone (GDH-PQQ). The GDH-PQQ based glucose monitoring systems may react with the maltose present in ORENCIA for intravenous administration, resulting in falsely elevated blood glucose readings on the day of infusion. When receiving intravenous ORENCIA, patients that require blood glucose monitoring should be advised to consider methods that do not react with maltose, such as those based on glucose dehydrogenase nicotine adenine dinucleotide (GDH-NAD), glucose oxidase, or glucose hexokinase test methods.

ORENCIA for subcutaneous administration does not contain maltose; therefore, patients do not need to alter their glucose monitoring.

8 USE IN SPECIFIC POPULATIONS

8.1 Pregnancy

Risk Summary

The data with ORENCIA use in pregnant women are insufficient to inform on drug-associated risk. However, there are clinical considerations for administering live vaccines to infants who were exposed to ORENCIA while in utero (see Clinical Considerations). In reproductive toxicology studies in rats and rabbits, no fetal malformations were observed with intravenous administration of ORENCIA during organogenesis at doses that produced exposures approximately 29 times the exposure at the maximum recommended human dose (MRHD) of 10 mg/kg/month on an AUC basis. However, in a pre- and postnatal development study in rats, ORENCIA altered immune function in female rats at 11 times the MRHD on an AUC basis.

Clinical Considerations

Infants and Administration of Live Vaccines

It is unknown if abatacept can cross the placenta into the fetus when a woman is treated with ORENCIA during pregnancy. Abatacept is an immunomodulatory agent. It is unknown if the immune response of an infant who was exposed in utero to abatacept and subsequently administered a live vaccine is impacted. Risks and benefits should be considered prior to vaccinating such infants [see Warnings and Precautions (5.4)].

Data

Human Data

There are no adequate and well-controlled studies of ORENCIA use in pregnant women. The data with ORENCIA use in pregnant women are insufficient to inform on drug-associated risk.

Animal Data

Intravenous administration of abatacept during organogenesis to mice (10, 55, or 300 mg/kg/day), rats (10, 45, or 200 mg/kg/day), and rabbits (10, 45, or 200 mg/kg every 3 days) produced exposures in rats and rabbits that were approximately 29 times the MRHD on an AUC basis (at maternal doses of 200 mg/kg/day in rats and rabbits), and no embryotoxicity or fetal malformations were observed in any species.

In a study of pre- and postnatal development in rats (10, 45, or 200 mg/kg every 3 days from gestation day 6 through lactation day 21), alterations in immune function in female offspring, consisting of a 9-fold increase in T-cell-dependent antibody response relative to controls on postnatal day (PND) 56 and thyroiditis in a single female pup on PND 112, occurred at approximately 11 times the MRHD on an AUC basis (at a maternal dose of 200 mg/kg). No adverse effects were observed at approximately 3 times the MRHD (a maternal dose of 45 mg/kg). It is not known if immunologic perturbations in rats are relevant indicators of a risk for development of autoimmune diseases in humans exposed in utero to abatacept. Exposure to abatacept in the juvenile rat, which may be more representative of the fetal immune system state in the human, resulted in immune system abnormalities including inflammation of the thyroid and pancreas [see Nonclinical Toxicology (13.2)].

8.2 Lactation

Risk Summary

There is no information regarding the presence of abatacept in human milk, the effects on the breastfed infant, or the effects on milk production. However, abatacept was present in the milk of lactating rats dosed with abatacept.

8.4 Pediatric Use

Polyarticular Juvenile Idiopathic Arthritis

The safety and effectiveness of ORENCIA for reducing signs and symptoms in patients 2 years of age and older with moderately to severely active polyarticular juvenile idiopathic arthritis (pJIA) have been established (ORENCIA may be used as monotherapy or concomitantly with methotrexate). Use of ORENCIA for this indication is supported by evidence from the following studies:

Intravenous Use: A randomized withdrawal efficacy, safety, and pharmacokinetic study of intravenous ORENCIA in 190 pediatric patients 6 to 17 years of age with pJIA [see Clinical Pharmacology (12.3) and Clinical Studies (14.2)]. Given that population pharmacokinetic (PK) analyses (after intravenous ORENCIA administration) showed that clearance of abatacept increased with baseline body weight, intravenous ORENCIA is administered either weight-based or weight ranged based [see Dosage and Administration (2.2)]. Intravenous ORENCIA administration has not been studied in patients younger than 6 years of age.
Subcutaneous Use: An open-label PK and safety study of subcutaneous ORENCIA in 205 pediatric patients aged 2 to 17 years old with pJIA, extrapolation of effectiveness of intravenous ORENCIA in patients with pJIA and subcutaneous ORENCIA in patients with RA [see Clinical Pharmacology (12.3) and Clinical Studies (14.2)]. Given that population PK analyses (after subcutaneous ORENCIA injection) in pJIA patients showed that there was a trend toward higher clearance of abatacept with increasing body weight, subcutaneous ORENCIA dosage is weight range-based [see Dosage and Administration (2.2)].

The safety and effectiveness of ORENCIA use in pJIA in pediatric patients less than two years of age have not been established.

Acute Graft Versus Host Disease Prophylaxis

The safety and effectiveness of ORENCIA for the prophylaxis of Acute Graft Versus Host Disease (aGVHD), in combination with a calcineurin inhibitor and methotrexate, in pediatric patients aged 2 years of age and older undergoing HSCT from a matched or 1 allele-mismatched unrelated donor have been established. Use of ORENCIA for this indication is supported by evidence from:

- adequate and well-controlled studies in adults and pediatric patients aged 6 years and older administered a dose of 10 mg/kg intravenously on the day before transplantation followed by a dose of 10 mg/kg intravenously on Days 5, 14, and 28 after transplantation and
- pharmacokinetic modeling and simulations of abatacept exposure in pediatric patients aged 2 to less than 6 years administered a dose of 15 mg/kg intravenously on the day before transplantation followed by a dose of 12 mg/kg intravenously on Days 5, 14, and 28 after transplantation.

Furthermore, the course of disease is sufficiently similar in pediatric patients aged 2 years to less than 6 years to that of patients aged 6 years and older to allow extrapolation of data to younger pediatric patients [see Clinical Pharmacology (12.3) and Clinical Studies (14.4)]. No new safety signals were observed in pediatric patients aged 6 years and older in Study GVHD-1.

The safety and effectiveness of ORENCIA for this indication have not been established in pediatric patients less than 2 years of age.

Psoriatic Arthritis

Subcutaneous Administration

The safety and effectiveness of subcutaneous ORENCIA have been established for treatment of psoriatic arthritis in pediatric patients 2 to 17 years old.

Use of ORENCIA in this age group is supported by evidence from adequate and well-controlled studies of ORENCIA in adults with PsA, pharmacokinetic data from adult patients with RA, adult patients with PsA, and pediatric patients with pJIA, and safety data from clinical studies in pediatric patients 2 to 17 years old with pJIA using the subcutaneous formulation.

The observed pre-dose (trough) concentrations are generally comparable between adults with RA and PsA and pediatric patients with JIA with active polyarthritis, and the PK exposure is expected to be comparable between adult PsA and pediatric patients with PsA. [see Adverse Reactions (6.1), Clinical Pharmacology (12.3), and Clinical Studies (14.1, 14.2, 14.3)].

The safety and effectiveness of subcutaneous ORENCIA have not been established in pediatric patients less than 2 years old with psoriatic arthritis.

Intravenous Administration

The safety and effectiveness of intravenous ORENCIA in pediatric patients with psoriatic arthritis have not been established.

Juvenile Animal Toxicity Data

A juvenile animal study conducted in rats dosed with abatacept from 4 to 94 days of age (prior to immune system maturity) showed an increase in the incidence of infections leading to death at all doses compared with controls. Altered T-cell subsets including increased T-helper cells and reduced T-regulatory cells were observed. In addition, inhibition of T-cell-dependent antibody responses (TDAR) was observed. Upon following these animals into adulthood, lymphocytic inflammation of the thyroid and pancreatic islets was observed. In contrast, studies in adult mice and monkeys have not demonstrated similar findings. As the immune system of the rat is undeveloped in the first few weeks after birth, the relevance of these results to humans is unknown.

8.5 Geriatric Use

Rheumatoid Arthritis

A total of 323 patients 65 years of age and older, including 53 patients 75 years and older, received ORENCIA in clinical studies. No overall differences in safety or effectiveness were observed between geriatric patients (patients aged 65 years of age and older) and younger adults, and other reported clinical experience has not identified differences in responses between geriatric patients and younger adults, but greater sensitivity of some geriatric patients cannot be ruled out. The frequency of serious infection and malignancy among ORENCIA-treated patients over age 65 was higher than for those under age 65. Because there is a higher incidence of infections and malignancies in the geriatric population in general, caution should be used when treating geriatric patients.

Acute Graft Versus Host Disease Prophylaxis

Of the 116 patients in Study GVHD-1 who received ORENCIA at a dose of 10 mg/kg for the prophylaxis of aGVHD, 12 (10%) were 65 years of age and older, and 2 (2%) patients were 75 years of age and older [see Clinical Studies (14.4)]. Clinical studies of ORENCIA for aGVHD did not include sufficient numbers of patients 65 years of age and older to determine whether they respond differently from younger adult patients.

10 OVERDOSAGE

ORENCIA doses up to 50 mg/kg (5 times the maximum recommended dose in patients aged 6 years and older and 3.3 times the maximum recommended dose in patients aged 2 to less than 6 years) have been administered intravenously without apparent toxic effect. In case of overdosage, it is recommended that the patient be monitored for any signs or symptoms of adverse reactions and appropriate symptomatic treatment instituted.

11 DESCRIPTION

Abatacept is a selective T-cell costimulation modulator. Abatacept is a soluble fusion protein that consists of the extracellular domain of human cytotoxic T-lymphocyte-associated antigen 4 (CTLA-4) linked to the modified Fc (hinge, CH2, and CH3 domains) portion of human immunoglobulin G1 (IgG1). Abatacept is produced by recombinant DNA technology in a mammalian cell expression system. The apparent molecular weight of abatacept is 92 kilodaltons.

ORENCIA (abatacept) for injection is a sterile, white, preservative-free lyophilized powder for reconstitution and dilution prior to intravenous infusion. Following reconstitution of the lyophilized powder with 10 mL of Sterile Water for Injection, USP, the reconstituted solution of ORENCIA is clear, colorless to pale yellow, with a concentration of 25 mg/mL and with a pH range of 7.2 to 7.8. Each single-dose vial of ORENCIA provides 250 mg abatacept, maltose (500 mg), monobasic sodium phosphate (17.2 mg), and sodium chloride (14.6 mg).

ORENCIA (abatacept) injection is a sterile, preservative-free, clear to slightly opalescent, colorless to pale-yellow solution with a pH range of 6.8 to 7.4 for subcutaneous administration. ORENCIA injection is supplied as a single-dose prefilled syringe or as a single-dose ClickJect autoinjector (see Table 6).

Table 6: Contents of ORENCIA Subcutaneous Injection
Presentation | Active Ingredient Quantity and Volume | Inactive Ingredient Content
ORENCIA injection 50 mg/0.4 mL prefilled syringe | 50 mg of abatacept in 0.4 mL of solution | dibasic sodium phosphate anhydrous (0.335 mg); monobasic sodium phosphate monohydrate (0.114 mg); poloxamer 188 (3.2 mg); sucrose (68 mg); qs to 0.4 mL Water for Injection, USP
ORENCIA injection 87.5 mg/0.7 mL prefilled syringe | 87.5 mg of abatacept in 0.7 mL of solution | dibasic sodium phosphate anhydrous (0.587 mg); monobasic sodium phosphate monohydrate (0.200 mg); poloxamer 188 (5.6 mg); sucrose (119 mg); qs to 0.7 mL Water for Injection, USP
ORENCIA injection 125 mg/mL prefilled syringe and ClickJect autoinjector | 125 mg of abatacept in 1 mL of solution | dibasic sodium phosphate anhydrous (0.838 mg); monobasic sodium phosphate monohydrate (0.286 mg); poloxamer 188 (8 mg); sucrose (170 mg); qs to 1 mL Water for Injection, USP

Unlike the lyophilized formulation for intravenous use, the ORENCIA solutions for subcutaneous administration contain no maltose.

12 CLINICAL PHARMACOLOGY

12.1 Mechanism of Action

Abatacept, a selective costimulation modulator, inhibits T-cell (T lymphocyte) activation by binding to CD80 and CD86, thereby blocking interaction with CD28. This interaction provides a costimulatory signal necessary for full activation of T lymphocytes. Activated T lymphocytes are implicated in the pathogenesis of RA, pJIA and PsA and are found in the synovium of patients with RA, pJIA and PsA.

In vitro, abatacept decreases T-cell proliferation and inhibits the production of the cytokines TNF alpha (TNFα), interferon-γ, and interleukin-2. In a rat collagen-induced arthritis model, abatacept suppresses inflammation, decreases anti-collagen antibody production, and reduces antigen specific production of interferon-γ. The relationship of these biological response markers to the mechanisms by which ORENCIA exerts its clinical effects is unknown.

12.2 Pharmacodynamics

In clinical trials with ORENCIA at doses approximating 10 mg/kg, decreases were observed in serum levels of soluble interleukin-2 receptor (sIL-2R), interleukin-6 (IL-6), rheumatoid factor (RF), C-reactive protein (CRP), matrix metalloproteinase-3 (MMP3), and TNFα. The relationship of these biological response markers to the mechanisms by which ORENCIA exerts its clinical effects is unknown.

No formal pharmacodynamic analyses of biologic response markers have been performed in patients exposed to ORENCIA as prophylaxis for aGVHD.

12.3 Pharmacokinetics

Healthy Adults and Adult RA - Intravenous Administration

The pharmacokinetics of abatacept were studied in healthy adult subjects after a single 10 mg/kg intravenous infusion and in RA patients after multiple 10 mg/kg intravenous infusions of ORENCIA (see Table 7).

Table 7: Pharmacokinetic Parameters (Mean, Range) in Healthy Subjects and RA Patients After 10 mg/kg ORENCIA Intravenous Infusion(s)
PK Parameter | Healthy Subjects (After 10 mg/kg Single Dose) n=13 | RA Patients (After 10 mg/kg Multiple Dosesa) n=14
Peak Concentration (Cmax) [mcg/mL] | 292 (175-427) | 295 (171-398)
Terminal half-life (t1/2) [days] | 16.7 (12-23) | 13.1 (8-25)
Systemic clearance (CL) [mL/h/kg] | 0.23 (0.16-0.30) | 0.22 (0.13-0.47)
Volume of distribution (Vss) [L/kg] | 0.09 (0.06-0.13) | 0.07 (0.02-0.13)
a Multiple intravenous infusions of ORENCIA were administered at days 1, 15, 30, and monthly thereafter.

The pharmacokinetics of abatacept in RA patients and healthy subjects appeared to be comparable. In RA patients, after multiple intravenous infusions, the pharmacokinetics of abatacept showed proportional increases of Cmax and AUC over the dose range of 2 mg/kg to 10 mg/kg. At 10 mg/kg, serum concentration appeared to reach a steady state by day 60 with a mean (range) trough concentration of 24 mcg/mL (1 to 66 mcg/mL). No systemic accumulation of abatacept occurred upon continued repeated treatment with 10 mg/kg at monthly intervals in RA patients.

Population pharmacokinetic analyses in RA patients revealed that there was a trend toward higher clearance of abatacept with increasing body weight. Age and gender (when corrected for body weight) did not affect clearance. Concomitant methotrexate, NSAIDs, corticosteroids, and TNF antagonists did not influence abatacept clearance.

No formal studies were conducted to examine the effects of either renal or hepatic impairment on the pharmacokinetics of abatacept.

Adult RA - Subcutaneous Administration

Abatacept exhibited linear pharmacokinetics following subcutaneous administration. The mean (range) for Cmin and Cmax at steady state observed after 85 days of treatment was 32.5 mcg/mL (6.6 to 113.8 mcg/mL) and 48.1 mcg/mL (9.8 to 132.4 mcg/mL), respectively. The bioavailability of abatacept following subcutaneous administration relative to intravenous administration was 79%. Mean estimates for systemic clearance (0.28 mL/h/kg), volume of distribution (0.11 L/kg), and terminal half-life (14.3 days) were comparable between subcutaneous and intravenous administration.

Study SC-2 was conducted to determine the effect of subcutaneous monotherapy use of ORENCIA on immunogenicity (without an intravenous loading dose) in 100 RA patients [see Adverse Reactions (6.3)]. In this study, a mean trough concentration of 12.6 mcg/mL was achieved after 2 weeks of dosing.

Consistent with the intravenous data, population pharmacokinetic analyses for subcutaneous ORENCIA in RA patients revealed that there was a trend toward higher clearance of abatacept with increasing body weight [see Dosage and Administration (2.1)]. Age and gender (when corrected for body weight) did not affect apparent clearance. Concomitant medication, such as methotrexate, corticosteroids, and NSAIDs, did not influence abatacept apparent clearance.

Polyarticular Juvenile Idiopathic Arthritis - Intravenous Administration

In Study JIA-1 among patients 6 to 17 years of age, the mean (range) steady state serum peak and trough concentrations of abatacept were 217 mcg/mL (57 to 700 mcg/mL) and 11.9 mcg/mL (0.15 to 44.6 mcg/mL) [see Clinical Studies (14.2)]. Population pharmacokinetic analyses of the serum concentration data showed that clearance of abatacept increased with baseline body weight [see Dosage and Administration (2.2)]. The estimated mean (range) clearance of abatacept in the juvenile idiopathic arthritis patients was 0.4 mL/h/kg (0.20 to 1.12 mL/h/kg). After accounting for the effect of body weight, the clearance of abatacept was not related to age and gender. Concomitant methotrexate, corticosteroids, and NSAIDs were also shown not to influence abatacept clearance.

Polyarticular Juvenile Idiopathic Arthritis - Subcutaneous Administration

In Study JIA-2 among patients 2 to 17 years of age, steady state of abatacept was achieved by Day 85 following the weekly body-weight–tiered subcutaneous ORENCIA dosing [see Clinical Studies (14.2)]. Comparable trough concentrations across weight tiers and age groups were achieved by the body-weight–tiered subcutaneous dosing regimen. The mean (range) trough concentration of abatacept at Day 113 was 44.4 mcg/mL (13.4 to 88.1 mcg/mL), 46.6 mcg/mL (22.4 to 97.0 mcg/mL), and 38.5 mcg/mL (9.3 to 73.2 mcg/mL) in pediatric JIA patients weighing 10 to <25 kg, 25 to <50 kg, and ≥50 kg, respectively.

Consistent with the intravenous data, population pharmacokinetic analyses for subcutaneous ORENCIA in JIA patients revealed that there was a trend toward higher clearance of abatacept with increasing body weight [see Dosage and Administration (2.2)]. Age and gender (when corrected for body weight) did not affect apparent clearance. Concomitant medication, such as methotrexate, corticosteroids, and NSAIDs, did not influence abatacept apparent clearance.

Adult Psoriatic Arthritis - Intravenous and Subcutaneous Administration

In Study PsA-I, a dose ranging study, intravenous ORENCIA was administered at 3 mg/kg, weight range-based dosing: 500 mg for patients weighing less than 60 kg, 750 mg for patients weighing 60 to 100 kg, and 1,000 mg for patients weighing greater than 100 kg, or doses of 30 mg/kg on Days 1 and 15 followed by weight-range-based dosing [see Clinical Studies (14.3)]. Following monthly intravenous ORENCIA administration, abatacept showed linear PK over the dose range in this study. At the weight-range-based dosing (see above), the steady state of abatacept was reached by Day 57 and the geometric mean (CV%) trough concentration (Cmin) was 24.3 mcg/mL (40.8%) at Day 169. In Study PsA-II following weekly subcutaneous administration of ORENCIA at 125 mg, the steady state of abatacept was reached at Day 57 and the geometric mean (CV%) Cmin was 25.6 mcg/mL (47.7%) at Day 169.

Consistent with the RA results, population pharmacokinetic analyses for abatacept in PsA patients revealed that there was a trend toward higher clearance (L/h) of abatacept with increasing body weight [see Dosage and Administration (2.3)]. In addition, relative to the RA patients with the same body weight, abatacept clearance in PsA patients was approximately 8% lower, resulting in higher abatacept exposures in patients with PsA. This slight difference in exposures, however, is not considered to be clinically meaningful.

Prophylaxis of Acute Graft versus Host Disease – Intravenous Administration

Table 8: Pharmacokinetic Parameters (Mean, Range) in Subjects Undergoing HSCT from a Matched or 1 Allele-Mismatched Unrelated Donor in Study GVHD-1
PK Parameter | 7 of 8 Cohort n=42 | 8 of 8 Cohort n=73
Minimum Concentration (Cmin) a [mcg/mL] | 59 (26-112) | 43 (25-73)
Peak Concentration (Cmax) [mcg/mL] | 221 (163-292) | 172 (107-254)
Terminal half-life (t1/2) [days] | 20.6 (6-43) | 20.8 (12-38)
Systemic clearance (CL) [mL/h/kg] | 0.26 (0.15-0.65) | 0.32 (0.18-0.56)
Volume of distribution (Vss) [L/kg] | 0.13 (0.08-0.27) | 0.17 (0.11-0.26)
a Cmin observed on Day 5 of the treatment period; n = 18 for the 7/8 Cohort; n = 32 for the 8/8 Cohort.
Cmax, t1/2, CL, and Vss are model predicted after first 10 mg/kg ORENCIA intravenous infusion.

In a study of patients who received ORENCIA for prophylaxis of acute Graft Versus Host Disease (aGVHD) aged 6 years and older, the geometric mean (%CV) trough concentrations (Cmin) of abatacept on Day 63 after transplant after 4 doses utilizing weight-based dosing of 10 mg/kg (maximum dose of 1,000 mg) administered on the day before transplantation (Day -1), followed by a dose on Day 5, 14, and 28 after transplant, were 22.5 mcg/mL (243.9 %CV) for recipients of 8 of 8 Human leukocyte antigen (HLA)-matched HSCTs from unrelated donors (URD), and 31.1 mcg/mL (114.4 %CV) for recipients of 7 of 8 HLA-matched HSCTs from unrelated donors (URD), respectively.

Population pharmacokinetic analyses in patients with aGVHD demonstrated that 7 of 8 HLA-matched HSCT recipients had 29% lower clearance compared to 8 of 8 HLA-matched HSCT recipients. Consistent with previous data, increasing body weight was associated with higher clearance of abatacept, while age (when corrected for body weight) did not affect apparent clearance. Concomitant medication, such as methotrexate and calcineurin inhibitors (e.g., cyclosporine and tacrolimus), did not influence abatacept clearance.

Based on population PK modeling and simulation with data from patients aged 6 and older, simulated exposures of abatacept following the first and last dose in pediatric subjects 2 to less than 6 years of age who received 15 mg/kg of ORENCIA via 60-minute intravenous infusion on Day -1, followed by 12 mg/kg via 60-minute intravenous infusion on Day 5, 14, and 28 are comparable to those in pediatric patients 6 to less than 17 years of age and adults patients who received 10 mg/kg via 60-minute intravenous infusion on Day -1, 5, 14, and 28.

13 NONCLINICAL TOXICOLOGY

13.1 Carcinogenesis, Mutagenesis, Impairment of Fertility

In a mouse carcinogenicity study, weekly subcutaneous injections of 20, 65, or 200 mg/kg of abatacept administered for up to 84 weeks in males and 88 weeks in females were associated with increases in the incidence of malignant lymphomas (all doses) and mammary gland tumors (intermediate- and high-dose in females). The mice from this study were infected with murine leukemia virus and mouse mammary tumor virus. These viruses are associated with an increased incidence of lymphomas and mammary gland tumors, respectively, in immunosuppressed mice. The doses used in these studies produced exposures 0.8, 2.0, and 3.0 times higher, respectively, than the exposure associated with the maximum recommended human dose (MRHD) of 10 mg/kg based on AUC (area under the time-concentration curve). The relevance of these findings to the clinical use of ORENCIA is unknown.

In a one-year toxicity study in cynomolgus monkeys, abatacept was administered intravenously once weekly at doses up to 50 mg/kg (producing 9 times the MRHD exposure based on AUC). Abatacept was not associated with any significant drug-related toxicity. Reversible pharmacological effects consisted of minimal transient decreases in serum IgG and minimal to severe lymphoid depletion of germinal centers in the spleen and/or lymph nodes. No evidence of lymphomas or preneoplastic morphologic changes was observed, despite the presence of a virus (lymphocryptovirus) known to cause these lesions in immunosuppressed monkeys within the time frame of this study. The relevance of these findings to the clinical use of ORENCIA is unknown.

No mutagenic potential of abatacept was observed in the in vitro bacterial reverse mutation (Ames) or Chinese hamster ovary/hypoxanthine guanine phosphoribosyl-transferase (CHO/HGPRT) forward point mutation assays with or without metabolic activation, and no chromosomal aberrations were observed in human lymphocytes treated with abatacept with or without metabolic activation.

Abatacept had no adverse effects on male or female fertility in rats at doses up to 200 mg/kg every three days (11 times the MRHD exposure based on AUC).

13.2 Animal Toxicology and/or Pharmacology

In studies of adult mice and monkeys, inhibition of TDAR was apparent. However, infection and mortality, altered T-helper cells, and inflammation of thyroid and pancreas were not observed.

14 CLINICAL STUDIES

14.1 Adult Rheumatoid Arthritis

Description of Clinical Studies of Intravenous ORENCIA for the Treatment of Patients with RA

The efficacy and safety of ORENCIA for intravenous administration were assessed in six randomized, double-blind, controlled studies (five placebo-controlled and one active-controlled) in patients ≥18 years of age with active RA diagnosed according to American College of Rheumatology (ACR) criteria. Studies I, II, III, IV, and VI required patients to have at least 12 tender and 10 swollen joints at randomization, and Study V did not require any specific number of tender or swollen joints. ORENCIA or placebo treatment was given intravenously at weeks 0, 2, and 4 and then every 4 weeks thereafter in Studies I, II, III, IV, and VI.

- Study I (NCT00279760) evaluated ORENCIA as monotherapy in 122 patients with active RA who had failed at least one non-biologic DMARD or etanercept.
- In Study II (NCT00162266) and Study III (NCT00048568), the efficacy of ORENCIA were assessed in patients with an inadequate response to MTX and who were continued on their stable dose of MTX.
- In Study IV (NCT00048581), the efficacy of ORENCIA was assessed in patients with an inadequate response to a TNF antagonist, with the TNF antagonist discontinued prior to randomization; other DMARDs were permitted.
- Study V (NCT00048932) primarily assessed safety in patients with active RA requiring additional intervention in spite of current therapy with DMARDs; all DMARDs used at enrollment were continued. Patients in Study V were not excluded for comorbid medical conditions.
- In Study VI (NCT00122382), the efficacy and safety of ORENCIA were assessed in methotrexate-naive patients with RA of less than 2 years disease duration. In Study VI, patients previously naive to methotrexate were randomized to receive ORENCIA plus methotrexate or methotrexate plus placebo.

Study I patients were randomized to receive one of three doses of ORENCIA (0.5, 2, or 10 mg/kg) or placebo ending at week 8. Study II patients were randomized to receive ORENCIA 2 or 10 mg/kg or placebo for 12 months. Study III, IV, V, and VI patients were randomized to receive a dose of ORENCIA based on weight range or placebo for 12 months (Studies III, V, and VI) or 6 months (Study IV). The dose of ORENCIA was 500 mg for patients weighing less than 60 kg, 750 mg for patients weighing 60 to 100 kg, and 1,000 mg for patients weighing greater than 100 kg.

Description of Clinical Studies of Subcutaneous or Intravenous ORENCIA for the Treatment of Patients with Adult RA

The efficacy of ORENCIA for subcutaneous administration were assessed in Study SC-1 (NCT00559585), which was a randomized, double-blind, double-dummy, non-inferiority study that compared ORENCIA administered subcutaneously to ORENCIA administered intravenously in 1457 patients with moderate to severely active RA, receiving background methotrexate (MTX), and experiencing an inadequate response to methotrexate (MTX-IR). In Study SC-1, patients were randomized with stratification by body weight (<60 kg, 60 to 100 kg, >100 kg) to receive (1) ORENCIA 125 mg subcutaneous injections weekly, after a single intravenous loading dose of ORENCIA based on body weight or (2) ORENCIA intravenously on Days 1, 15, 29, and every four weeks thereafter. Subjects continued taking their current dose of MTX from the day of randomization.

Clinical Response in Adult RA Patients

The percent of ORENCIA-treated patients achieving ACR 20, 50, and 70 responses and major clinical response in Studies I, III, IV, and VI are shown in Table 9. ORENCIA-treated patients had higher ACR 20, 50, and 70 response rates at 6 months compared to placebo-treated patients. Month 6 ACR response rates in Study II for the 10 mg/kg group were similar to the ORENCIA group in Study III.

In Studies III and IV, improvement in the ACR 20 response rate versus placebo was observed within 15 days in some patients and within 29 days versus MTX in Study VI. In Studies II, III, and VI, ACR response rates were maintained to 12 months in ORENCIA-treated patients. ACR responses were maintained up to three years in the open-label extension of Study II. In Study III, ORENCIA-treated patients experienced greater improvement than placebo-treated patients in morning stiffness.

In Study VI, a greater proportion of patients treated with ORENCIA plus MTX achieved a low level of disease activity as measured by a DAS28-CRP less than 2.6 at 12 months compared to those treated with MTX plus placebo (Table 9). Of patients treated with ORENCIA plus MTX who achieved DAS28-CRP less than 2.6, 54% had no active joints, 17% had one active joint, 7% had two active joints, and 22% had three or more active joints, where an active joint was a joint that was rated as tender or swollen or both.

In Study SC-1, the main outcome measure was ACR 20 at 6 months. The pre-specified non-inferiority margin was a treatment difference of −7.5%. As shown in Table 10, the study demonstrated non-inferiority of ORENCIA administered subcutaneously to intravenous infusions of ORENCIA with respect to ACR 20 responses up to 6 months of treatment. ACR 50 and 70 responses are also shown in Table 9. No major differences in ACR responses were observed between intravenous and subcutaneous treatment groups in subgroups based on weight categories (less than 60 kg, 60 to 100 kg, and more than 100 kg; data not shown).

Table 9: Clinical Responses in Controlled Trials in Patients with RA
 | Percent of Patients
 | Intravenous Administration |  |  |  |  |  |  |  | Subcutaneous or Intravenous Administration
 | Inadequate Response to DMARDs |  | Inadequate Response to Methotrexate (MTX) |  | Inadequate Response to TNF Antagonists |  | MTX-Naive |  | Inadequate Response to MTX
 | Study I |  | Study III |  | Study IV |  | Study VI |  | Study SC-1
Response Rate | ORNa n=32 | PBO n=32 | ORNb +MTX n=424 | PBO +MTX n=214 | ORNb + DMARDs n=256 | PBO + DMARDs n=133 | ORNb +MTX n=256 | PBO +MTX n=253 | ORNe SC +MTX n=693 | ORNe IV +MTX n=678
ACR 20
Month 3 | 53% | 31% | 62%‡ | 37% | 46%‡ | 18% | 64%* | 53% | 68% | 69%
Month 6 | NA | NA | 68%‡ | 40% | 50%‡ | 20% | 75%† | 62% | 76%§ | 76%
Month 12 | NA | NA | 73%‡ | 40% | NA | NA | 76%‡ | 62% | NA | NA
ACR 50
Month 3 | 16% | 6% | 32%‡ | 8% | 18%† | 6% | 40%‡ | 23% | 33% | 39%
Month 6 | NA | NA | 40%‡ | 17% | 20%‡ | 4% | 53%‡ | 38% | 52% | 50%
Month 12 | NA | NA | 48%‡ | 18% | NA | NA | 57%‡ | 42% | NA | NA
ACR 70
Month 3 | 6% | 0 | 13%‡ | 3% | 6%* | 1% | 19%† | 10% | 13% | 16%
Month 6 | NA | NA | 20%‡ | 7% | 10%† | 2% | 32%† | 20% | 26% | 25%
Month 12 | NA | NA | 29%‡ | 6% | NA | NA | 43%‡ | 27% | NA | NA
Major Clinical Responsec | NA | NA | 14%‡ | 2% | NA | NA | 27%‡ | 12% | NA | NA
DAS28-CRP <2.6d
Month 12 | NA | NA | NA | NA | NA | NA | 41%‡ | 23% | NA | NA
* p<0.05, ORENCIA (ORN) vs placebo (PBO) or MTX.
† p<0.01, ORENCIA vs placebo or MTX.
‡ p<0.001, ORENCIA vs placebo or MTX.
§ 95% CI: −4.2, 4.8 (based on prespecified margin for non-inferiority of −7.5%).
a 10 mg/kg.
b Dosing based on weight range [see Dosage and Administration (2.1)].
c Major clinical response is defined as achieving an ACR 70 response for a continuous 6-month period.
d Refer to text for additional description of remaining joint activity.
e Per protocol data is presented in table. For ITT; n=736, 721 for SC and IV ORENCIA, respectively.

The results of the components of the ACR response criteria for Studies III, IV, and SC-1 are shown in Table 10 (results at Baseline [BL] and 6 months [6 M]). In ORENCIA-treated patients, greater improvement was seen in all ACR response criteria components through 6 and 12 months than in placebo-treated patients.

Table 10: Components of ACR Responses at 6 Months in Adult Patients with RA
 | Intravenous Administration |  |  |  |  |  |  |  | Subcutaneous or Intravenous Administration
 | Inadequate Response to MTX |  |  |  | Inadequate Response to TNF Antagonists |  |  |  | Inadequate Response to MTX
 | Study III |  |  |  | Study IV |  |  |  | Study SC-1c
 | ORN +MTX n=424 |  | PBO +MTX n=214 |  | ORN +DMARDs n=256 |  | PBO +DMARDs n=133 |  | ORN SC +MTX n=693 |  | ORN IV +MTX n=678
Component (median) | BL | 6 M | BL | 6 M | BL | 6 M | BL | 6 M | BL | 6 M | BL | 6 M
Number of tender joints (0-68) | 28 | 7‡ | 31 | 14 | 30 | 13‡ | 31 | 24 | 27 | 5 | 27 | 6
Number of swollen joints (0-66) | 19 | 5‡ | 20 | 11 | 21 | 10‡ | 20 | 14 | 18 | 4 | 18 | 3
Paina | 67 | 27‡ | 70 | 50 | 73 | 43† | 74 | 64 | 71 | 25 | 70 | 28
Patient global assessmenta | 66 | 29‡ | 64 | 48 | 71 | 44‡ | 73 | 63 | 70 | 26 | 68 | 27
Disability indexb | 1.75 | 1.13‡ | 1.75 | 1.38 | 1.88 | 1.38‡ | 2.00 | 1.75 | 1.88 | 1.00 | 1.75 | 1.00
Physician global assessmenta | 69 | 21‡ | 68 | 40 | 71 | 32‡ | 69 | 54 | 65 | 16 | 65 | 15
CRP (mg/dL) | 2.2 | 0.9‡ | 2.1 | 1.8 | 3.4 | 1.3‡ | 2.8 | 2.3 | 1.6 | 0.7 | 1.8 | 0.7
† p<0.01, ORENCIA (ORN) vs placebo (PBO), based on mean percent change from baseline.
‡ p<0.001, ORENCIA vs placebo, based on mean percent change from baseline.
a Visual analog scale: 0 = best, 100 = worst.
b Health Assessment Questionnaire: 0 = best, 3 = worst; 20 questions; 8 categories: dressing and grooming, arising, eating,
walking, hygiene, reach, grip, and activities.
c SC-1 is a non-inferiority study. Per protocol data is presented in table.

The percent of patients achieving the ACR 50 response for Study III by visit is shown in Figure 1. The time course for the ORENCIA group in Study VI was similar to that in Study III.

Figure 1: Percent of Patients Achieving ACR 50 Response by Visit* (Study III)

*The same patients may not have responded at each time point.

The percent of patients achieving the ACR 50 response for Study SC-1 in the ORENCIA subcutaneous (SC) and intravenous (IV) treatment arms at each treatment visit was as follows: Day 15—SC 3%, IV 5%; Day 29—SC 11%, IV 14%; Day 57—SC 24%, IV 30%; Day 85—SC 33%, IV 38%; Day 113—SC 39%, IV 41%; Day 141—SC 46%, IV 47%; Day 169—SC 51%, IV 50%.

Radiographic Response in Adult RA Patients

In Study III and Study VI, structural joint damage was assessed radiographically and expressed as change from baseline in the Genant-modified Total Sharp Score (TSS) and its components, the Erosion Score (ES) and Joint Space Narrowing (JSN) score. ORENCIA/MTX slowed the progression of structural damage compared to placebo/MTX after 12 months of treatment as shown in Table 11.

Table 11: Mean Radiographic Changes in Study IIIa and Study VIb
Parameter | ORENCIA/MTX | Placebo/MTX | Differences | P-valued
Study III
First Year
TSS | 1.07 | 2.43 | 1.36 | <0.01
ES | 0.61 | 1.47 | 0.86 | <0.01
JSN score | 0.46 | 0.97 | 0.51 | <0.01
Second Year
TSS | 0.48 | 0.74c | - | -
ES | 0.23 | 0.22c | - | -
JSN score | 0.25 | 0.51c | - | -
Study VI
First Year
TSS | 0.6 | 1.1 | 0.5 | 0.04
a Patients with an inadequate response to MTX.
b MTX-naive patients.
c Patients received 1 year of placebo/MTX followed by 1 year of ORENCIA/MTX.
d Based on a nonparametric ANCOVA model.

In the open-label extension of Study III, 75% of patients initially randomized to ORENCIA/MTX and 65% of patients initially randomized to placebo/MTX were evaluated radiographically at Year 2. As shown in Table 11, progression of structural damage in ORENCIA/MTX-treated patients was further reduced in the second year of treatment.

Following 2 years of treatment with ORENCIA/MTX, 51% of patients had no progression of structural damage as defined by a change in the TSS of zero or less compared with baseline. Fifty-six percent (56%) of ORENCIA/MTX-treated patients had no progression during the first year compared to 45% of placebo/MTX-treated patients. In their second year of treatment with ORENCIA/MTX, more patients had no progression than in the first year (65% vs 56%).

Physical Function Response and Health-Related Outcomes in Adult RA Patients

Improvement in physical function was measured by the Health Assessment Questionnaire Disability Index (HAQ-DI). In the HAQ-DI, ORENCIA demonstrated greater improvement from baseline versus placebo in Studies II-V and versus MTX in Study VI. In Study SC-1, improvement from baseline as measured by HAQ-DI at 6 months and over time was similar between subcutaneous and intravenous ORENCIA administration. The results from Studies II and III are shown in Table 12. Similar results were observed in Study V compared to placebo and in Study VI compared to MTX. During the open-label period of Study II, the improvement in physical function has been maintained for up to 3 years.

Table 12: Mean Improvement from Baseline in Health Assessment Questionnaire Disability Index (HAQ-DI) in Adult Patients with RA
 | Inadequate Response to Methotrexate
 | Study II |  | Study III
HAQ Disability Index | ORENCIAa +MTX (n=115) | Placebo +MTX (n=119) | ORENCIAb +MTX (n=422) | Placebo +MTX (n=212)
Baseline (Mean) | 0.98c | 0.97c | 1.69d | 1.69d
Mean Improvement Year 1 | 0.40c,*** | 0.15c | 0.66d,*** | 0.37d
*** p<0.001, ORENCIA vs placebo.
a 10 mg/kg.
b Dosing based on weight range [see Dosage and Administration (2.1)].
c Modified Health Assessment Questionnaire: 0 = best, 3 = worst; 8 questions; 8 categories: dressing and grooming, arising, eating, walking, hygiene, reach, grip, and activities.
d Health Assessment Questionnaire: 0 = best, 3 = worst; 20 questions; 8 categories: dressing and grooming, arising, eating, walking, hygiene, reach, grip, and activities.

Health-related quality of life was assessed by the SF-36 questionnaire at 6 months in Studies II, III, and IV and at 12 months in Studies II and III. In these studies, improvement was observed in the ORENCIA group as compared with the placebo group in all 8 domains of the SF-36 as well as the Physical Component Summary (PCS) and the Mental Component Summary (MCS).

14.2 Polyarticular Juvenile Idiopathic Arthritis

Polyarticular Juvenile Idiopathic Arthritis - Intravenous Administration

The safety and efficacy of ORENCIA with intravenous administration were assessed in Study JIA-1 (NCT00095173), a three-part study including an open-label extension in pediatric patients with polyarticular juvenile idiopathic arthritis (pJIA). Patients 6 to 17 years of age (n=190) with moderately to severely active pJIA who had an inadequate response to one or more DMARDs, such as MTX or TNF antagonists, were treated. Patients had a disease duration of approximately 4 years with moderately to severely active disease at study entry, as determined by baseline counts of active joints (mean, 16) and joints with loss of motion (mean, 16); patients had elevated C-reactive protein (CRP) levels (mean, 3.2 mg/dL) and ESR (mean, 32 mm/h). The patients enrolled had JIA subtypes that at disease onset included oligoarticular (16%), polyarticular (64%; 20% were rheumatoid factor positive), and systemic JIA without systemic manifestations (20%). At study entry, 74% of patients were receiving MTX (mean dose, 13.2 mg/m^2 per week) and remained on a stable dose of MTX (those not receiving MTX did not initiate MTX treatment during the study).

In Period A (open-label, lead-in), patients received 10 mg/kg (maximum 1,000 mg per dose) intravenously on days 1, 15, 29, and monthly thereafter. Response was assessed utilizing the ACR Pediatric 30 definition of improvement, defined as ≥30% improvement in at least 3 of the 6 JIA core set variables and ≥30% worsening in not more than 1 of the 6 JIA core set variables. Patients demonstrating an ACR Pedi 30 response at the end of Period A were randomized into the double-blind phase (Period B) and received either ORENCIA or placebo for 6 months or until disease flare. Disease flare was defined as a ≥30% worsening in at least 3 of the 6 JIA core set variables with ≥30% improvement in not more than 1 of the 6 JIA core set variables; ≥2 cm of worsening of the Physician or Parent Global Assessment was necessary if used as 1 of the 3 JIA core set variables used to define flare, and worsening in ≥2 joints was necessary if the number of active joints or joints with limitation of motion was used as 1 of the 3 JIA core set variables used to define flare.

At the conclusion of Period A, pediatric ACR 30/50/70 responses were 65%, 50%, and 28%, respectively. Pediatric ACR 30 responses were similar in all subtypes of JIA studied.

During the double-blind randomized withdrawal phase (Period B), ORENCIA-treated patients (intravenous) experienced significantly fewer disease flares compared to placebo-treated patients (20% vs 53%); 95% CI of the difference (15%, 52%). The risk of disease flare among patients continuing on intravenous ORENCIA was less than one-third than that for patients withdrawn from intravenous ORENCIA treatment (hazard ratio=0.31, 95% CI [0.16, 0.59]). Among patients who received intravenous ORENCIA throughout the study (Period A, Period B, and the open-label extension Period C), the proportion of pediatric ACR 30/50/70 responders has remained consistent for 1 year.

Polyarticular Juvenile Idiopathic Arthritis - Subcutaneous Administration

ORENCIA for subcutaneous administration without an intravenous loading dose was assessed in Study JIA-2 (NCT01844518), a 2-period, open-label study that included pediatric patients 2 to 17 years of age (n=205). Patients had active polyarticular disease at the time of the study and had inadequate response to at least one nonbiologic or biologic DMARD. The JIA patient subtypes at study entry included polyarticular (79%; 22% were rheumatoid factor positive), extended and persistent oligoarticular (14%), enthesitis-related arthritis (1%), and systemic JIA without systemic manifestations (2%). Patients had a mean disease duration of 2.5 years with active joints (mean, 11.9), joints with loss of motion (mean, 10.4), and elevated C-reactive protein (CRP) levels (mean, 1.2 mg/dL). At study entry, 80% of patients were receiving MTX and remained on a stable dose of MTX. Patients received weekly open-label ORENCIA subcutaneously by a weight-tiered dosing regimen. The primary objective of the study was evaluation of PK in order to support the extrapolation of efficacy based on exposure to ORENCIA supported by descriptive efficacy [see Clinical Pharmacology (12.3)].

JIA ACR 30/50/70 responses assessed at 4 months in the 2- to 17-year-old patients treated with subcutaneous ORENCIA were consistent with the results from intravenous ORENCIA in Study JIA-1.

14.3 Psoriatic Arthritis

The efficacy of ORENCIA was assessed in 594 adult patients (18 years and older) with psoriatic arthritis (PsA), in two randomized, double-blind, placebo-controlled studies (Studies PsA-I [NCT00534313] and PsA-II [NCT01860976]). Patients had active PsA (≥3 swollen joints and ≥3 tender joints) despite prior treatment with DMARD therapy and had one qualifying psoriatic skin lesion of at least 2 cm in diameter. In PsA-I and PsA-II, 37% and 61% of patients, respectively, were treated with TNF antagonists previously.

During the initial 24-week, double-blind period of Study PsA-I, 170 patients were randomized to receive one of four intravenous treatments on Days 1, 15, 29, and then every 28 days (there was no escape during the 24-week period):

- Placebo
- ORENCIA 3 mg/kg
- ORENCIA 500 mg for patients weighing less than 60 kg, ORENCIA 750 mg for patients weighing 60 to 100 kg, and ORENCIA 1,000 mg for patients weighing greater than 100 kg (weight-range-based dosing), or
- ORENCIA 30 mg/kg on Days 1 and 15 followed by weight range-based ORENCIA dosing (i.e., 500 mg for patients weighing less than 60 kg, 750 mg for patients weighing 60 to 100 kg, and 1,000 mg for patients weighing greater than 100 kg).

After the 24-week double blind period in Study PsA-I, patients received open-label intravenous ORENCIA every 28 days.

Patients were allowed to receive stable doses of concomitant MTX, low dose corticosteroids (equivalent to ≤10 mg of prednisone) and/or NSAIDs during the trial. At enrollment, approximately 60% of patients were receiving MTX. At baseline, the mean (SD) CRP for ORENCIA IV was 17 mg/L (33.0) and mean number (SD) of tender joints and swollen joints was 22.2 (14.3) and 10.9 (7.6), respectively.

In PsA-II, 424 patients were randomized 1:1 to receive weekly doses of subcutaneous placebo or ORENCIA 125 mg without a loading dose for 24 weeks-in a double-blind manner, followed by open-label subcutaneous ORENCIA 125 mg weekly. Patients were allowed to receive stable doses of concomitant MTX, sulfasalazine, leflunomide, hydroxychloroquine, low dose corticosteroids (equivalent to ≤10 mg of prednisone) and/or NSAIDs during the trial. At randomization, 60% of patients were receiving MTX. The baseline disease characteristics included presence of joint erosion on X-rays in 84% (341/407) with a mean (SD) PsA-modified Sharp van der Heijde erosion score (SHS) of 10.8 (24.2), elevated serum C reactive protein (CRP) in 66% [277/421]) with a mean (SD) of 14.1 mg/L (25.9), and polyarticular disease in 98% (416/424) of patients with a mean number (SD) of tender joints and swollen joints of 20.2 (13.3) and 11.6 (7.5), respectively. Patients who had not achieved at least a 20% improvement from baseline in their swollen and tender joint counts by Week 16 escaped to open-label subcutaneous ORENCIA 125 mg weekly.

The primary endpoint for both PsA-I and PsA-II was the proportion of patients achieving ACR 20 response at Week 24 (Day 169).

Clinical Response in Adults with PsA

A greater proportion of adult patients with PsA achieved an ACR 20 response after treatment with intravenous ORENCIA (weight-range-based dosing as described above) compared to placebo in Study PsA-I and a greater proportion of adult patients with PsA achieved an ACR 20 response after treatment with subcutaneous 125 mg compared to placebo in Study PsA-II at Week 24. Responses were seen regardless of prior TNF antagonist treatment and regardless of concomitant non-biologic DMARD treatment. The percent of patients achieving ACR 20, 50, or 70 responses in Studies PsA‑I and PsA-II are presented in Table 13 below.

Table 13: Proportion of Patients With ACR Responses at Week 24 in Studies PsA-I and PsA-IIa
 | PsA-I |  | PsA-II
 | ORENCIA Weight-Range-Based Intravenous Dosingb N=40 | Placebo N=42 | ORENCIA 125 mg Subcutaneous N=213 | Placebo N=211
ACR 20 | 47.5%* | 19.0% | 39.4%* | 22.3%
ACR 50 | 25.0% | 2.4% | 19.2% | 12.3%
ACR 70 | 12.5% | 0% | 10.3% | 6.6%
* p<0.05 versus placebo.
a Patients who had less than 20% improvement in tender or swollen joint counts at Week 16 met escape criteria and were considered non-responders.
b Weight range-based intravenous dosing: ORENCIA 500 mg for patients weighing less than 60 kg, ORENCIA 750 mg for patients weighing 60 to 100 kg, and ORENCIA 1,000 mg for patients weighing greater than 100 kg.

The percentage of patients in PsA-II achieving ACR 20 response through Week 24 is shown below in Figure 2.

Figure 2: Percent of Patients Achieving ACR 20 Responsea in PsA-II Study Through Week 24 (Day 169)

Results were generally consistent across the ACR components in Study PsA-I and PsA-II.

Improvements in enthesitis and dactylitis were seen with ORENCIA treatment at Week 24 in both PsA-I and PsA-II.

Physical Function Response in Adults with PsA

In study PsA-I, there was a higher proportion of patients with at least a 0.30 decrease from baseline in Health Assessment Questionnaire-Disability Index (HAQ-DI) score at Week 24, with an estimated difference for ORENCIA weight range-based dosing as described above (45%) vs. placebo (19%) of 26.1 (95% confidence interval: 6.8, 45.5). In study PsA-II, the proportion of patients with at least a 0.35 decrease from baseline in HAQ-DI on ORENCIA was 31%, as compared to 24% on placebo (estimated difference: 7%; 95% confidence interval: -1%, 16%). There was a higher adjusted mean change from baseline in HAQ-DI on ORENCIA (-0.33) vs. placebo (-0.20) at Week 24, with an estimated difference of -0.13 (95% confidence interval: -0.25, -0.01).

14.4 Prophylaxis of Acute Graft versus Host Disease

Study GVHD-1

The efficacy of ORENCIA, in combination with a calcineurin inhibitor (CNI) and methotrexate (MTX), for the prophylaxis of Acute Graft Versus Host Disease (aGVHD), was evaluated in a multicenter, two cohort clinical study (GVHD-1, NCT01743131) in patients age 6 years and older who underwent hematopoietic stem cell transplantation (HSCT) from a matched or 1 allele-mismatched unrelated donor (URD). The two cohorts in GVHD-1 included:

1) an open-label, single-arm study of 43 patients who underwent a 7 of 8 Human Leukocyte Antigen (HLA)-matched HSCT (7 of 8 cohort); and
2) a randomized (1:1), double-blind, placebo-controlled study of patients who underwent an 8 of 8 HLA-matched HSCT who received ORENCIA or placebo in combination with a CNI and MTX (8 of 8 cohort).

In both the 7/8 and 8/8 cohorts, ORENCIA was administered at a dose of 10 mg/kg (1,000 mg maximum dose) as an intravenous infusion over 60 minutes, beginning on the day before transplantation (Day -1), followed by administration on Days 5, 14, and 28 after transplantation. Baseline demographic and clinical characteristics of both the 7 of 8 and 8 of 8 cohorts are outlined below in Table 14.

Table 14: Baseline Demographic and Clinical Characteristics: 7 of 8 and 8 of 8 Cohort Treated Analysis Population in Study GVHD-1
 | 7 of 8 Cohort | 8 of 8 Cohort
 | ORENCIA (+ CNI and MTX) N=43 | ORENCIA (+ CNI and MTX) N=73 | Placebo (+CNI and MTX) N=69
Age - Median | 38 | 44 | 40
Age - Range | 6-76 | 6-71 | 7-74
Gender - Male | 27 (63) | 41 (56) | 37 (54)
White | 31 (72) | 63 (86) | 61 (88)
Black or African American | 7 (16) | 3 (4.1) | 2 (2.9)
Asian | 2 (4.7) | 4 (6) | 2 (2.9)
Hispanic | 7 (16) | 4 (6) | 2 (2.9)
Malignancy type
Acute Myeloid Leukemia (AML) | 15 (35) | 30 (41) | 22 (32)
Myelodysplastic Syndrome (MDS) | 11 (26) | 15 (21) | 12 (17)
Acute Lymphoblastic Leukemia (ALL) | 8 (19) | 20 (27) | 22 (32)
Acute leukemia or ambiguous lineage | 1 (2.3) | 0 | 1 (1.4)
Hodgkin and Non-Hodgkin lymphoma | 1 (2.3) | 1 (1.4) | 1 (1.4)
Acute Lymphoblastic Lymphoma in 2nd or Greater Complete Remission | 1 (2.3) | 4 (6) | 1 (1.4)
Chronic Myelomonocytic leukemia | 1 (2.3) | 1 (1.4) | 4 (6)
Chronic Myelogenous leukemia | 4 (9) | 1 (1.4) | 5 (7)
Not reported | 1 (2.3) | 1 (1.4) | 1 (1.4)
GVHD Prophylaxis
Cyclosporine | 16 (37) | 11 (15) | 11 (16)
Tacrolimus | 27 (63) | 62 (85) | 58 (84)
Type of Graft
Bone Marrow | 21 (49) | 33 (45) | 26 (38)
Cytokine Mobilized Peripheral Blood (PBSC) | 22 (51) | 40 (55) | 43 (62)
Conditioning Regimen
TBI and Chemotherapy | 11 (26) | 20 (27) | 26 (38)
Busulfan and Cyclophosphamide | 13 (30) | 28 (38) | 21 (30)
Busulfan and Fludarabine | 8 (19) | 7 (10) | 2 (2.9)
Melphalan and Fludarabine | 11 (26) | 18 (25) | 20 (29)

Efficacy was established based on overall survival (OS) and grade II-IV aGVHD free survival (GFS) results assessed at Day 180 post-transplantation. ORENCIA + CNI and MTX did not significantly improve grade III-IV GFS versus placebo + CNI and MTX at Day 180 post-transplantation. The efficacy results of the GVHD-1 8 of 8 cohort are shown in Table 15.

Table 15: Efficacy Results in 8 of 8 Cohort in Study GVHD-1 at Day 180 Post-Transplantation
Endpoint | ORENCIA; (+CNI and MTX); n=73 | Placebo; (+CNI and MTX); n=69
Gr III-IV aGVHD Free Survivala Rate (95% CI) | 87% (77%, 93%) | 75% (63%, 84%)
Hazard Ratio (95% CI) | 0.55 (0.26, 1.18)
Gr II-IV aGVHD Free Survivalb Rate (95% CI) | 50% (38%, 61%) | 32% (21%, 43%)
Hazard Ratio (95% CI) | 0.54 (0.35, 0.83)
Overall Survival Rate (95% CI) | 97% (89%, 99%) | 84% (73%, 91%)
Hazard Ratio (95% CI) | 0.33 (0.12, 0.93)
a Gr III-IV aGVHD Free Survival was measured from the date of transplantation until the onset of documented Grade III-IV aGVHD, or death by any cause up to Day 180 post-transplantation.
b Gr II-IV aGVHD Free Survival was measured from the date of transplantation until the onset of documented Grade II-IV aGVHD, or death by any cause up to Day 180 post-transplantation.

In an exploratory analysis of the 7 of 8 cohort of ORENCIA-treated patients (n=43), the rates of Grade III-IV GVHD-free survival, Grade II-IV GVHD-free survival, and overall survival at day 180 post-transplantation were 95% (95% CI 83%, 99%), 53% (95% CI 38%, 67%), and 98% (95% CI 85%, 100%), respectively.

Study GVHD-2

GVHD-2 (NCT05421299) was a clinical study that used data from the Center for International Blood and Marrow Transplant Research (CIBMTR). The study analyzed outcomes of ORENCIA in combination with a CNI and MTX, versus a CNI and MTX alone, for the prophylaxis of aGVHD, in patients 6 years of age or older who underwent HSCT from a 1 allele-mismatched URD between 2011 and 2018. The ORENCIA + CNI and MTX-treated group (n=54) included 42 patients from GVHD-1, in addition to 12 patients treated with ORENCIA outside of GVHD-1. The comparator group (n=162) was randomly selected in a 3:1 ratio to the ORENCIA-treated group from the CIBMTR registry from patients who had not received ORENCIA during the study period. Analyses used propensity score matching and inverse probability of treatment weighting to help address the impact of selection bias.

Efficacy was based on Overall Survival (OS) at Day 180 post-HSCT. The OS rate at Day 180 in the ORENCIA in combination with CNI and MTX group was 98% (95% CI: 78, 100) and the OS rate at Day 180 in the CNI and MTX group was 75% (95% CI: 67, 82).

16 HOW SUPPLIED/STORAGE AND HANDLING

For Intravenous Infusion

ORENCIA® (abatacept) for injection is a white lyophilized powder for intravenous infusion after reconstitution and dilution. It is supplied as an individually packaged, single-dose vial (one may use less than the full contents of the vial or use more than one vial) with a silicone-free disposable syringe, providing 250 mg of abatacept:

NDC 0003-2187-13: in a carton presentation

For Subcutaneous Use

ORENCIA® (abatacept) injection and ORENCIA® ClickJect (abatacept) injection are clear to slightly opalescent, colorless to pale yellow solutions for subcutaneous administration.

Prefilled Syringe

ORENCIA (abatacept) injection, 50 mg/0.4 mL, 87.5 mg/0.7 mL, and 125 mg/mL, is supplied as single-dose disposable prefilled glass syringes with BD UltraSafe Passive™ needle guard and flange extenders.

The Type I glass syringe has a coated stopper and fixed stainless steel needle (5 bevel, 29-gauge thin wall, ½-inch needle) covered with a rigid needle shield. The prefilled syringe provides ORENCIA in the following packages:

NDC 0003-2814-11 (50 mg/0.4 mL): pack of 4 syringes with a passive needle safety guard

NDC 0003-2818-11 (87.5 mg/0.7 mL): pack of 4 syringes with a passive needle safety guard

NDC 0003-2188-11 (125 mg/mL): pack of 4 syringes with a passive needle safety guard

ClickJect Autoinjector

ORENCIA (abatacept) ClickJect, 125 mg/mL, is supplied as a single-dose disposable prefilled autoinjector. The Type I glass syringe contained in the autoinjector has a coated stopper and fixed stainless steel needle (5 bevel, 27-gauge special thin wall, ½-inch needle) covered with a rigid needle shield. The autoinjector provides 125 mg of abatacept in 1 mL and is provided in the following package:

NDC 0003-2188-51: pack of 4 autoinjectors

Storage

Refrigerate ORENCIA lyophilized powder supplied in a vial at 2°C to 8°C (36°F to 46°F). Do not use beyond the expiration date on the vial. Protect the vials from light by storing in the original package until time of use.

Refrigerate ORENCIA solution supplied in a prefilled syringe or ClickJect autoinjector at 2°C to 8°C (36°F to 46°F). Do not use beyond the expiration date on the prefilled syringe or autoinjector. Protect from light by storing in the original package until time of use. Do not allow the prefilled syringe or autoinjector to freeze.

17 PATIENT COUNSELING INFORMATION

Advise the patient to read the FDA-approved patient labeling (Patient Information and Instructions for Use).

Increased Risk of Infection with Concomitant Use With Immunosuppressants for RA

Inform patients that the concomitant use with other immunosuppressives (e.g., biologic DMARDs, JAK inhibitors) is not recommended [see Warnings and Precautions (5.1) and Drug Interactions (7.1)].

Hypersensitivity Reactions

Instruct patients to immediately tell their healthcare professional if they experience symptoms of an allergic reaction on the day of administration or the day after ORENCIA administration [see Warnings and Precautions (5.2)].

Infections

Inform patients that serious infections have been reported in patients receiving ORENCIA [see Warnings and Precautions (5.3)].

Immunizations

Inform patients that live vaccines should not be given concurrently with ORENCIA or within 3 months of its discontinuation [see Warnings and Precautions (5.4)].

Blood Glucose Testing

Maltose is contained in ORENCIA for intravenous administration and can give falsely elevated blood glucose readings with certain blood glucose monitors on the day of ORENCIA infusion. Advise patients treated with intravenous ORENCIA who are using GDH-PQQ-based monitoring systems for glucose (e.g., diabetics) to consider using other methods for glucose monitoring. This recommendation is not applicable to patients treated with subcutaneous ORENCIA [see Drug Interactions (7.2)].

Disposal of Prefilled Syringes and ClickJect Autoinjectors

Advise patients to follow disposal instructions in the Instructions for Use. A puncture-resistant container for disposal of needles and syringes should be used. Instruct patients that they will need to follow their community guidelines for the correct way to dispose of their sharps disposal container. Instruct patients not to recycle their used sharps disposal container.

Bristol-Myers Squibb Company
Princeton, New Jersey 08543 USA
U.S. License Number 1713

PATIENT INFORMATION

ORENCIA® (oh-REN-see-ah)
(abatacept)
injection, for intravenous or subcutaneous use

What is ORENCIA?
ORENCIA is a prescription medicine that reduces signs and symptoms in:

- adults with moderate to severe rheumatoid arthritis (RA), including those who have not been helped enough by other medicines for RA. ORENCIA may prevent further damage to your bones and joints and may help your ability to perform daily activities. In adults, ORENCIA may be used alone or with other RA treatments other than tumor necrosis factor (TNF) antagonists.
- people 2 years of age and older with moderate to severe polyarticular juvenile idiopathic arthritis (pJIA). ORENCIA may be used alone or with methotrexate.
- people 2 years of age and older with active psoriatic arthritis (PsA). In adults, ORENCIA can be used alone or with other PsA treatments. In children, ORENCIA can be used alone or with methotrexate.

ORENCIA is also used for the preventative treatment of acute graft versus host disease (aGVHD), in combination with a calcineurin inhibitor and methotrexate, in:

- people 2 years of age and older undergoing hematopoietic stem cell transplantation (HSCT) from a matched or 1 allele-mismatched unrelated-donor.

It is not known if ORENCIA is safe and effective in children less than two years of age for the treatment of pJIA.

It is not known if ORENCIA is safe and effective in children less than two years of age for the treatment of PsA.

It is not known if ORENCIA is safe and effective in children less than two years of age for the preventative treatment of aGVHD.

Before you receive or use ORENCIA, tell your healthcare provider about all of your medical conditions, including if you:

- have any kind of infection even if it is small (such as an open cut or sore), or an infection that is in your whole body (such as the flu). If you have an infection during treatment with ORENCIA, you may have a higher chance for getting serious side effects.
- have an infection that will not go away or an infection that keeps coming back.
- are allergic to abatacept or any of the ingredients in ORENCIA. See the end of this Patient Information leaflet for a complete list of ingredients in ORENCIA.
- have or have had inflammation of your liver due to an infection (viral hepatitis). Your healthcare provider may examine you for hepatitis before treatment with ORENCIA.
- have had a lung infection called tuberculosis (TB), a positive skin test for TB, or you recently have been in close contact with someone who has had TB. Your healthcare provider may examine you for TB or perform a skin test before treatment with ORENCIA. Symptoms of TB may include:

- a cough that does not go away
- weight loss

- fever
- night sweats

- have a history of Epstein-Barr Virus (EBV) or Cytomegalovirus (CMV) in people receiving ORENCIA for preventative treatment of aGVHD during HSCT from an unrelated donor.
- are scheduled to have surgery.
- recently received a vaccination or are scheduled for a vaccination.
- have a history of a breathing problem called chronic obstructive pulmonary disease (COPD).
- have diabetes and use a blood glucose monitor to check your blood sugar (blood glucose) levels.

- ORENCIA for intravenous infusion (given through a needle placed in a vein) contains maltose, a type of sugar, that can give false high blood sugar readings with certain types of blood glucose monitors on the day of ORENCIA infusion. Your healthcare provider may tell you to use a different way to monitor your blood sugar levels.
- ORENCIA for subcutaneous injection (injected under the skin) does not contain maltose. You do not need to change your blood sugar monitoring if you are using ORENCIA subcutaneously.

- are pregnant or plan to become pregnant. It is not known if ORENCIA can harm your unborn baby. If you took ORENCIA during pregnancy, talk to your healthcare provider before your baby receives any vaccines.

- are breastfeeding or plan to breastfeed. It is not known if ORENCIA passes into your breast milk. Talk to your healthcare provider about the best way to feed your baby if you use ORENCIA.
- Some people treated with ORENCIA have developed skin cancer. Tell your healthcare provider if you have a family or personal history of skin cancer, and if you see any growths or changes in the appearance of your skin during or after your treatment with ORENCIA.

Tell your healthcare provider about all the medicines you take, including prescription and over-the-counter medicines, vitamins, and herbal supplements.

ORENCIA may affect the way other medicines work, and other medicines may affect the way ORENCIA works causing serious side effects.

Especially tell your healthcare provider if you take other biologic medicines that may affect your immune system, such as:

- Enbrel® (etanercept)
- Humira® (adalimumab)
- Remicade® (infliximab)

- Kineret® (anakinra)
- Rituxan® (rituximab)
- Simponi® (golimumab)

- Cimzia® (certolizumab pegol)
- Actemra® (tocilizumab)

You may have a higher chance of getting a serious infection if you take ORENCIA with other biologic medicines that may affect your immune system.

Know the medicines you take. Keep a list of them to show your healthcare provider and pharmacist when you get a new prescription.

How will I receive or use ORENCIA?

For treatment of RA, pJIA or PsA:

- You may receive ORENCIA given by a healthcare provider through a vein in your arm (intravenous infusion). It takes about 30 minutes to give you the full dose of medicine. You will then receive ORENCIA 2 weeks and 4 weeks after the first dose and then every 4 weeks. Intravenous administration of ORENCIA is not approved for pediatric patients with psoriatic arthritis.
- You may also receive ORENCIA as an injection under your skin (subcutaneous). For home use, ORENCIA comes in a prefilled syringe or prefilled ClickJect autoinjector. Your healthcare provider will prescribe the type that is best for you. If your healthcare provider decides that you or a caregiver can give your injections of ORENCIA prefilled syringes or ORENCIA ClickJect autoinjectors at home, you or your caregiver should receive training on the right way to prepare and inject ORENCIA. Do not try to inject ORENCIA until you have been shown the right way to give the injections by your healthcare provider.
- Your healthcare provider will tell you how much ORENCIA to use and when to use it.

See the Instructions for Use at the end of this Patient Information leaflet for instructions about the right way to prepare and give your ORENCIA injections at home.

For preventative treatment of aGVHD:

- You will receive ORENCIA by a healthcare provider through a vein in your arm (intravenous infusion) over 60 minutes on the day before transplantation (Day -1). You will then receive ORENCIA on Days 5, 14, and 28 after transplantation.
- Your healthcare provider may give you antiviral medicines before, during, and after your transplantation to help prevent Epstein-Barr Virus (EBV) and Cytomegalovirus (CMV) infections.

What are the possible side effects of ORENCIA?

ORENCIA may cause serious side effects, including:

- infections. ORENCIA can make you more likely to get infections or make the infection that you have get worse. Some people have died from these infections. Call your healthcare provider right away if you have any symptoms of an infection. Symptoms of an infection may include:

- fever
- feel very tired
- have a cough

- have flu-like symptoms
- warm, red, or painful skin

- allergic reactions. Allergic reactions can happen to people who are treated with ORENCIA. Call your healthcare provider or go to the emergency room right away if you have any symptoms of an allergic reaction. Symptoms of an allergic reaction may include:

- hives
- swollen face, eyelids, lips, or tongue

- trouble breathing

- hepatitis B infection in people who carry the virus in their blood. If you are a carrier of the hepatitis B virus (a virus that affects the liver), the virus can become active during treatment with ORENCIA. Your healthcare provider may do a blood test before you start treatment with ORENCIA.
- vaccinations. You should not receive ORENCIA with certain types of vaccines (live vaccines). You can receive non-live vaccines, such as pneumococcal and inactivated influenza (flu) vaccines. ORENCIA may also cause some vaccinations to be less effective. Talk with your healthcare provider about your vaccination plans.
- breathing problems in people with Chronic Obstructive Pulmonary Disease (COPD). You may get certain respiratory problems more often if you receive ORENCIA and have COPD. Symptoms of respiratory problems include:

- COPD that becomes worse
- cough

- trouble breathing

- cancer (malignancies). Certain kinds of cancer have been reported in people using ORENCIA. It is not known if ORENCIA increases your chance of getting certain kinds of cancer.
- Cytomegalovirus (CMV) and Epstein-Barr Virus (EBV) infections. CMV and EBV infections and return of CMV and EBV (reactivation) have happened in people receiving ORENCIA for preventative treatment of aGVHD during unrelated HSCT. Your healthcare provider will monitor you for 6 months after transplantation and may treat you with medicines to help prevent CMV and EBV infection if needed.

The most common side effects of ORENCIA in people with RA include:

- headache
- upper respiratory tract infection

- sore throat
- nausea

In children and adolescents, other side effects may include:

- diarrhea
- cough

- fever
- abdominal pain

The most common side effects of ORENCIA in prevention of aGVHD include:

- low red blood cell count
- high blood pressure
- CMV infection
- fever
- pneumonia

- nosebleed
- decreased CD4 lymphocytes
- increased levels of magnesium in the blood
- kidney problems

These are not all the possible side effects of ORENCIA.

Call your doctor for medical advice about side effects. You may report side effects to FDA at 1-800-FDA-1088.

How should I store ORENCIA?

- Store ORENCIA in the refrigerator at 36°F to 46°F (2°C to 8°C).
- Keep ORENCIA in the original package and out of the light.
- Do not freeze ORENCIA.
- Safely throw away medicine that is out of date or no longer needed.

Keep ORENCIA and all medicines out of the reach of children.

General information about the safe and effective use of ORENCIA.

Medicines are sometimes prescribed for purposes other than those listed in a Patient Information leaflet. Do not use ORENCIA for a condition for which it was not prescribed. Do not give ORENCIA to other people, even if they have the same symptoms that you have. It may harm them.

You can ask your pharmacist or healthcare provider for information about ORENCIA that is written for health professionals.

What are the ingredients in ORENCIA?

Active ingredient: abatacept

Intravenous inactive ingredients: maltose, monobasic sodium phosphate, sodium chloride for administration

Subcutaneous inactive ingredients: sucrose, poloxamer 188, monobasic sodium phosphate monohydrate, dibasic sodium phosphate anhydrous, water for injection.

Bristol-Myers Squibb Company
Princeton, NJ 08543 USA, U.S. License Number 1713

All other trademarks are property of their respective owners.

For more information, go to www.ORENCIA.com or call 1-800-ORENCIA.

This Patient Information has been approved by the U.S. Food and Drug Administration.
Revised: 5/2024

Instructions for Use

ORENCIA® (oh-REN-see-ah)
(abatacept)
Prefilled syringe with BD UltraSafe Passive™ needle guard

ORENCIA® prefilled syringe with
BD UltraSafe Passive™ needle guard

(abatacept) Injection

Read these instructions before you start using your ORENCIA prefilled syringe and each time you get a refill. There may be new information. Before you use the prefilled syringe for the first time, make sure your healthcare provider shows you the right way to use it and decides that you or a caregiver may be able to give your injections of ORENCIA at home.

Important:

- Keep the prefilled syringe in the refrigerator until ready to use.
- Do not freeze.

Before you begin: get to know your prefilled syringe

There are 3 types of prefilled syringes:

The type of prefilled syringe you receive depends on the dose prescribed by your healthcare provider.

The 125 mg/mL prefilled syringe is shown below.

Before use

After use

The prefilled syringe has a flange extender that makes it easier to hold and inject, and a needle guard that automatically covers the needle after a complete injection.

- Do not remove the needle cover until you are ready to inject.
- Do not pull back on the plunger at any time.
- Do not recap the prefilled syringe at any time, as this may damage, bend, or break the needle.

Go to Step 1

Step 1: Preparing for an ORENCIA injection

Gather and place supplies for your injection on a clean, flat surface.

Only the prefilled syringe is included in the package:

Alcohol
  swab

Prefilled syringe with
  UltraSafe Passive needle guard

Adhesive
  bandage

Sharps disposal container

Cotton ball or gauze

Let your prefilled syringe warm up.

Remove 1 prefilled syringe from the refrigerator and wait 30 minutes to allow it to reach room temperature.

- Do not speed up the warming process in any way, such as using the microwave or placing the syringe in warm water.
- Do not remove the needle cover while allowing the prefilled syringe to reach room temperature.

Wash your hands well with soap and water.

Go to Step 2

Step 2: Examine the prefilled syringe

Hold the prefilled syringe by the body with the needle cover pointing down as shown.

- Check the expiration date printed on the label.
  Do not use if the expiration date has passed.
- Check the prefilled syringe for damage.
  Do not use if it is cracked or broken.

Check the Liquid.

- Check the liquid in the prefilled syringe through the viewing window. It should be clear and colorless to pale yellow.

- Do not inject if the liquid is cloudy, discolored, or has particles in it.

Note: the 50 mg prefilled syringe is shown.

Note: It is normal to see an air bubble. Do not attempt to remove it.

Go to Step 3

Step 3: Check the dose on the prefilled syringe

Hold the syringe at eye level. Look closely to make sure that the amount of liquid in the prefilled syringe is at or just above the fill line for your prescribed dose:

Do not use if your prefilled syringe does not have the correct amount of liquid. Call your pharmacist immediately.

Go to Step 4

Step 4: Choose and prepare an injection site

Choose your injection site.

Choose your injection site in either the stomach (abdomen), front of the thighs, or outer area of upper arm (only if caregiver administered).

Rotate injection site.

- Each week you can use the same area of your body but use a different injection site in that area.

- Do not inject into an area where the skin is tender, bruised, red, scaly, or hard. Do not give the injection in any areas with scars or stretch marks.
- Record the date, time, and site where you inject.

Gently clean injection site.

- Wipe the injection site with an alcohol swab and let it air dry.
- Do not touch the injection site again before giving the injection.
- Do not fan or blow on the clean area.

Remove the needle cover by holding the body of the prefilled syringe with one hand and pulling the cover straight off with your other hand.

Do not put the needle cover back on the needle after you remove it. Throw away the needle cover in your household trash.

- Do not use the prefilled syringe if it is dropped after the needle cover is removed.
- Do not use the prefilled syringe if the needle is damaged or bent.

Note: It is normal to see a drop of fluid leaving the needle.

- Do not recap the prefilled syringe, as this may damage the needle.

Go to Step 5

Step 5: Inject Your Dose of ORENCIA

Hold the body of the prefilled syringe in your hand using your thumb and index finger. With your other hand, pinch the area of skin you cleaned.

Insert the needle.

Gently insert the needle into the pinched skin at a 45° angle.

Complete all steps to deliver your full dose of the medicine.

Inject: push the plunger with your thumb as far as it will go.

Release the needle guard: slowly lift your thumb from the plunger to activate the needle guard.

Confirm: after a complete injection, the needle guard will cover the needle and you may hear a click.

Remove the prefilled syringe and let go of the pinched skin.

Go to Step 6

Step 6: After the injection

Care of injection site:; - There may be a little bleeding at the injection site. You can press a cotton ball or gauze over the injection site. - Do not rub the injection site. - If needed, you may cover the injection site with an adhesive bandage.
Throwing away (disposing of) used prefilled syringes:
- Put your used ORENCIA prefilled syringes in a FDA-cleared sharps disposal container right away after use. Do not throw away (dispose of) loose needles and prefilled syringes in your household trash.
- If you do not have a FDA-cleared sharps disposal container, you may use a household container that is:
 | - made of a heavy-duty plastic, - can be closed with a tight-fitting, puncture-resistant lid, without sharps being able to come out, - upright and stable during use, - leak resistant, and - properly labeled to warn of hazardous waste inside the container.
- When your sharps disposal container is almost full, you will need to follow your community guidelines for the right way to dispose of your sharps disposal container. There may be state or local laws about how you should throw away used needles and syringes. For more information about safe sharps disposal, and for specific information about sharps disposal in the state that you live in, go to the FDA’s website at: http://www.fda.gov/safesharpsdisposal.
- Do not throw away (dispose of) your used sharps disposal container in your household trash unless your community guidelines permit this. Do not recycle your used sharps disposal container.
See Frequently Asked Questions for additional throwing away (disposal) information.; If your injection is administered by a caregiver, this person must also be careful handling the syringe to prevent accidental needle stick injury and possibly spreading infection.; Keep the ORENCIA prefilled syringes and the sharps disposal container out of the reach of children.
How to store ORENCIA prefilled syringe
- Store ORENCIA in the refrigerator at 36°F to 46°F (2°C to 8°C).
- Keep ORENCIA in the original package and out of the light.
- Do not freeze ORENCIA.
- Safely throw away medicine that is out of date or no longer needed.
Go to next page
Frequently Asked Questions
Q. |  | Why do I need to allow the prefilled syringe to warm up at room temperature for 30 minutes prior to injecting?
A. |  | This step is primarily for your comfort. Never try to speed up the warming process in any way, like using the microwave or placing the syringe in warm water.
Q. |  | Is it necessary to hold the skin pinch during the entire time I inject the dose?
A. |  | You must pinch the skin during needle insertion however, for your comfort you may release the skin pinch as you deliver the injection.
Q. |  | What if my prefilled syringe appears to be broken or damaged?
A. |  | Do not use the prefilled syringe. Contact your healthcare provider or pharmacist for further instructions.
Q. |  | What if I cannot clearly see the liquid inside the syringe?
A. |  | Look at the syringe closely by holding at eye level and up to the light. You may tilt the syringe slowly to get a better view of the drug fluid. If you still have trouble, contact your healthcare provider or pharmacist for further instructions.
Q. |  | Is it normal to feel a little bit of burning or pain during injection?
A. |  | You may feel a prick from the needle. Sometimes, the medicine can cause slight irritation near the injection site. Discomfort should be mild to moderate. If you have any side effects, including pain, swelling, or discoloration near the injection site, contact your healthcare provider.
Go to next page
Frequently Asked Questions
Q. |  | How should I dispose of a used prefilled syringe?
A. |  | Place the used prefilled syringe into an FDA-cleared sharps disposal container.; If you do not have one you may use a household container that is:; - made of a heavy-duty plastic, - can be closed with a tight-fitting, puncture-resistant lid, without sharps being able to come out, - upright and stable during use, leak-resistant, and properly labeled to warn of hazardous waste inside the container. - When your sharps disposal container is almost full, you will need to follow your community guidelines for the right way to dispose of your sharps disposal container. There may be state or local laws about how you should throw away used needles and injector pens. For more information about safe sharps disposal, and for specific information about sharps disposal in the state that you live in, go to the FDA’s website at: http://www.fda.gov/safesharpsdisposal.
Q. |  | How should I keep my prefilled syringes cool while traveling?
A. |  | Store them in a cool carrier between 36ºF to 46ºF (2ºC to 8ºC). Do not freeze them. Keep them in the original carton and protected from light. Your healthcare provider may know about special carrying cases.
Q. |  | Can I take my prefilled syringes on an airplane?
A. |  | Generally, you are allowed to carry your prefilled syringes with you on an airplane. Do not put them in your checked luggage. You should carry your prefilled syringes with you in your travel cooler at a temperature of 36ºF to 46ºF (2ºC to 8ºC). Keep your prefilled syringes in the original carton, and with its original preprinted labels and protected from light.
Q. |  | What if my prefilled syringe does not stay cool for an extended period of time? Is it dangerous to use?
A. |  | Contact 1-800-673-6242 for more information.
Go to back cover
If you have questions or concerns about your prefilled syringe, please contact your healthcare provider or call our toll-free help line at 1-800-673-6242.

Bristol-Myers Squibb Company
Princeton, NJ 08543 USA, U.S. License Number 1713

This Instructions for Use has been approved by the U.S. Food and Drug Administration.

ORENCIA is a registered trademark of Bristol-Myers Squibb Company.
BD UltraSafe Passive™ is a trademark of Becton, Dickinson, and Company.

Revised 10/2023

Instructions for Use

ORENCIA® ClickJect™ (oh-REN-see-ah)
(abatacept)
Prefilled autoinjector

ORENCIA® ClickJect™

(abatacept) injection

Prefilled autoinjector

125 mg/mL, single-dose autoinjector, for subcutaneous use only

Read these instructions before you use the ClickJect autoinjector and each time you get a refill. There may be new information. Before you use the autoinjector for the first time, make sure your healthcare provider shows you the right way to use it.

Important:

- Keep the ClickJect autoinjector in the refrigerator until ready to use.
- Do not freeze.

Before you begin:

Get to know the ClickJect autoinjector

- The autoinjector automatically delivers the medicine. The transparent tip locks over the needle when the injection is complete and the autoinjector is removed from the skin.
- Do not remove the orange needle cover until you are ready to inject.

Before use

After use

Gather supplies for your injection on a clean, flat surface
(only the ClickJect autoinjector is included in the package):

Alcohol
  swab

ClickJect
  autoinjector

Adhesive
  bandage

Sharps disposal container

Cotton ball or gauze

Go to Step 1

Step 1: Prepare your autoinjector

Let your ClickJect autoinjector warm up.

Remove 1 autoinjector from the refrigerator and let it rest at room temperature for 30 minutes.

Do not remove the autoinjector needle cover while allowing it to reach room temperature.

Wash your hands well with soap and water.

Examine the ClickJect autoinjector:

- Check expiration date printed on the label.
  Do not use if past the expiration date.
- Check the autoinjector for damage.
  Do not use if it is cracked or broken.
- Check the liquid through the viewing window. It should be clear and colorless to pale yellow. You may see a small air bubble. You do not need to remove it. Do not inject if the liquid is cloudy, discolored, or has particles in it.

Go to Step 2

Step 2: Prepare for injection

Choose your injection site
in either the stomach (abdomen), front of the thighs, or outer area of upper arm (only if caregiver administered).

Rotate injection site.

- Each week you can use the same area of your body but use a different injection site in that area.
- Do not inject into an area where the skin is tender, bruised, red, scaly, or hard. Do not give the injection in any areas with scars or stretch marks.
- Record the date, time, and site where you inject.

Gently clean injection site:

- Wipe the injection site with an alcohol swab and let it air dry.
- Do not touch the injection site again before giving the injection.
- Do not fan or blow on the clean area.

Pull orange needle cover straight off.

- Do not twist the needle cover.
- Do not recap the autoinjector.
- Throw away (discard) the needle cover in your
  household trash.
- Do not use the autoinjector if it is dropped after the needle cover is removed.
  Note: It is normal to see a drop of fluid leaving the needle.

Go to Step 3

Step 3: Inject your dose

Position the autoinjector so you can see the viewing window and it is at a 90° angle to the injection site. With your other hand, gently pinch the cleaned skin.

Complete all steps to deliver your full dose of medicine:

Push down
on the skin to unlock
the autoinjector.

Press button, hold for 15 seconds and watch the window.

- You will hear a click as the injection begins.
- To deliver the full dose of medicine, hold the autoinjector in place for 15 seconds and wait until the blue indicator stops moving in the window.

Remove the ClickJect autoinjector from the injection site by lifting it straight up. After you remove it from your skin, the transparent tip will lock over the needle. Release the pinched skin.

Go to Step 4

Step 4: After the injection

Care of injection site:; - There may be a little bleeding at the injection site. You can press a cotton ball or gauze over the injection site. - Do not rub the injection site. - If needed, you may cover the injection site with an adhesive bandage.
Throwing away (disposing of) used ClickJect autoinjectors:
- Put your used ClickJect autoinjector in a FDA-cleared sharps disposal container right away after use. Do not throw away (dispose of) loose needles and prefilled syringes in your household trash.
- If you do not have a FDA-cleared sharps disposal container, you may use a household container that is:
 | - made of a heavy-duty plastic, - can be closed with a tight-fitting, puncture-resistant lid, without sharps being able to come out, - upright and stable during use, - leak resistant, and - properly labeled to warn of hazardous waste inside the container.
- When your sharps disposal container is almost full, you will need to follow your community guidelines for the right way to dispose of your sharps disposal container. There may be state or local laws about how you should throw away used needles and syringes. For more information about safe sharps disposal, and for specific information about sharps disposal in the state that you live in, go to the FDA’s website at: http://www.fda.gov/safesharpsdisposal.
- Do not dispose of your used sharps disposal container in your household trash unless your community guidelines permit this. Do not recycle your used sharps disposal container.
See Frequently Asked Questions for additional throwing away (disposal) information.; If your injection is administered by a caregiver, this person must also handle the autoinjector carefully to prevent accidental needle stick injury and possibly spreading infection.
Keep autoinjector and the sharps disposal container out of the reach of children.
How to store ORENCIA ClickJect autoinjector
- Store ORENCIA in the refrigerator at 36°F to 46°F (2°C to 8°C).
- Keep ORENCIA in the original package and out of the light.
- Do not freeze ORENCIA.
- Safely throw away medicine that is out of date or no longer needed.
Continued on next page
Frequently Asked Questions
Q. |  | Why do I need to allow the autoinjector to warm up at room temperature for 30 minutes prior to injecting?
A. |  | This step is primarily for your comfort. If the medicine is cold, the injection may take longer than 15 seconds. Never try to speed the warming process in any way, like using the microwave or placing the autoinjector in warm water.
Q. |  | What if I accidentally remove the needle cover (orange cap) before I’m ready to use the autoinjector?
A. |  | If you remove the cover before you are ready to use the autoinjector, be careful. Do not try to replace it. Use the autoinjector as soon as possible. While you prepare for the injection, carefully place the autoinjector on its side on a clean, flat surface. Be sure to keep the autoinjector away from children.
Q. |  | What if the autoinjector appears to be broken or damaged?
A. |  | Do not use the autoinjector. Contact your healthcare provider or pharmacist for further instructions.
Q. |  | What if the injection was not triggered?
A. |  | Before the injection can be triggered, the device must be unlocked. To unlock, firmly push the autoinjector down on the skin without touching the button. When the stop-point is felt, the device is unlocked and can be triggered by pushing the button.
Q. |  | I feel a little bit of burning or pain during injection. Is this normal?
A. |  | When giving an injection, you may feel a prick from the needle. Sometimes, the medicine can cause slight irritation near the injection site. If this occurs, the discomfort should be mild to moderate. If you experience any side effects, including pain, swelling, or discoloration near the injection site, contact your healthcare provider or pharmacist immediately. You are encouraged to report side effects of prescription drugs to the FDA. Visit www.fda.gov/medwatch or call 1-800-FDA-1088.
Q. |  | How do I know I received my full dose?
A. |  | Before lifting the autoinjector from the injection site, check to make sure that the blue indicator has stopped moving. Then, before throwing away (disposing of) the autoinjector, check the bottom of the transparent viewing window to make sure there is no liquid left inside. If the medicine has not been completely injected, consult your healthcare provider or pharmacist.
Continued on next page
Frequently Asked Questions
Q. |  | How should I throw away (dispose of) a used autoinjector?
A. |  | Place used autoinjector into an FDA-cleared sharps disposal container right away after use.; - If you do not have one, you may use a household container that is:
 |  |  | - made of a heavy-duty plastic, - can be closed with a tight-fitting, puncture-resistant lid, without sharps being able to come out, - upright and stable during use, leak-resistant, and properly labeled to warn of hazardous waste inside the container.
 |  | - When your sharps disposal container is almost full, you will need to follow your community guidelines for the right way to throw away (dispose of) your sharps disposal container. There may be state or local laws about how you should throw away used needles and Autoinjectors. For more information about safe sharps disposal, and for specific information about sharps disposal in the state that you live in, go to the FDA’s website at: http://www.fda.gov/safesharpsdisposal. - Do not recycle your used sharps disposal container.
Q. |  | How should I keep my autoinjector cool while traveling?
A. |  | Your healthcare provider or pharmacist may be familiar with special carrying cases for injectable medicines. Store in the refrigerator at 36°F to 46°F (2°C to 8°C). Do not freeze. Protect from light.
Q. |  | Can I take my autoinjector on board an aircraft?
A. |  | Generally, this is allowed. Be sure to pack your autoinjector in your carry-on, and do not put it in your checked luggage. You should carry it with you in your travel cooler at a temperature of 36°F to 46°F (2°C to 8°C) until you are ready to use it. Airport security procedures and airline policies change from time to time, so it’s best to check with airport authorities and the airline for any special rules. Prior to flying, get a letter from your healthcare provider to explain that you are traveling with prescription medicine that uses a device with a needle; if you are carrying a sharps container in your carry-on baggage, notify the screener at the airport.
Q. |  | What if my autoinjector does not stay cool for an extended period of time? Is it dangerous to use?
A. |  | Contact 1-800-673-6242 for details.
If you have questions or concerns about your autoinjector, please contact a healthcare provider or call our toll-free help line at 1-800-673-6242.

Bristol-Myers Squibb Company
Princeton, NJ 08543 USA, U.S. License Number 1713

This Instructions for Use has been approved by the U.S. Food and Drug Administration.

ORENCIA is a registered trademark and ClickJect is a trademark of Bristol-Myers Squibb Company.

Revised 1/2024

ORENCIA 250 mg/vial for Injection Representative Packaging

See How Supplied section for a complete list of available packages of ORENCIA.

Rx only
NDC 0003-2187-13
ORENCIA®
(abatacept)
Lyophilized Powder for IV Infusion
250 mg/vial
ONLY USE THE SILICONE-FREE DISPOSABLE SYRINGE INCLUDED IN THE PACKAGE FOR RECONSTITUTION
Bristol-Myers Squibb Company
Princeton, New Jersey 08543 USA
US License No. 1713

ORENCIA 50 mg/0.4 mL Injection Representative Packaging

Bristol-Myers Squibb
NDC 0003-2814-11
4 Single-Dose Prefilled Syringes with BD UltraSafe Passive™ Needle Guard
ORENCIA®
(abatacept)
Injection
50 mg/0.4mL
Single-Dose Prefilled Syringe with BD UltraSafe Passive™ Needle Guard
FOR SUBCUTANEOUS USE ONLY
WARNING: Keep out of reach of children
Discard each syringe after use
Rx only

ORENCIA 87.5 mg/0.7 mL Injection Representative Packaging

Bristol-Myers Squibb
NDC 0003-2818-11
4 Single-Dose Prefilled Syringes with BD UltraSafe Passive™ Needle Guard
ORENCIA®
(abatacept)
Injection
87.5 mg/0.7mL
Single-Dose Prefilled Syringe with BD UltraSafe Passive™ Needle Guard
FOR SUBCUTANEOUS USE ONLY
WARNING: Keep out of reach of children
Discard each syringe after use
Rx only

ORENCIA 125 mg/mL Injection Representative Packaging

Bristol-Myers Squibb
NDC 0003-2188-11
4 Single-Dose Prefilled Syringes with BD UltraSafe Passive™ Needle Guard
ORENCIA®
(abatacept)
Injection
125 mg/mL
Single-Dose Prefilled Syringe with BD UltraSafe Passive™ Needle Guard
FOR SUBCUTANEOUS USE ONLY
WARNING: Keep out of reach of children
Discard each syringe after use
Rx only

ORENCIA 125 mg/mL ClickJect Representative Packaging

Bristol-Myers Squibb
NDC 0003-2188-51
4 Single-Dose Prefilled Autoinjectors
ORENCIA® ClickJect™
(abatacept)
Injection
125 mg/mL
Single-Dose Autoinjector
FOR SUBCUTANEOUS USE ONLY
Refrigerate immediately
WARNING: Keep out of reach of children
Discard each autoinjector after use
Open from this side Rx only